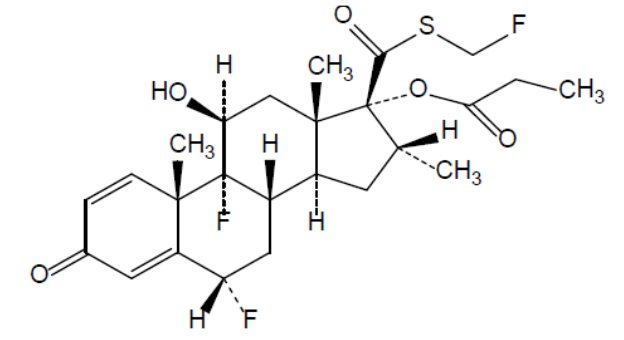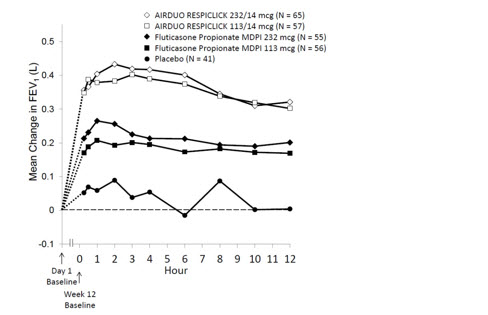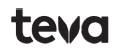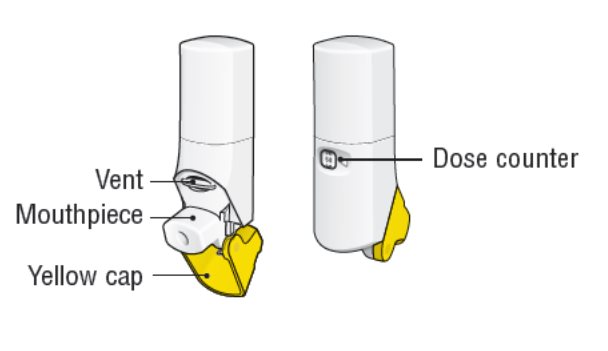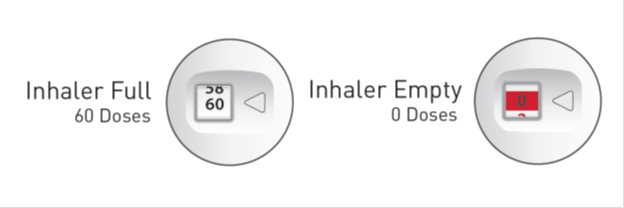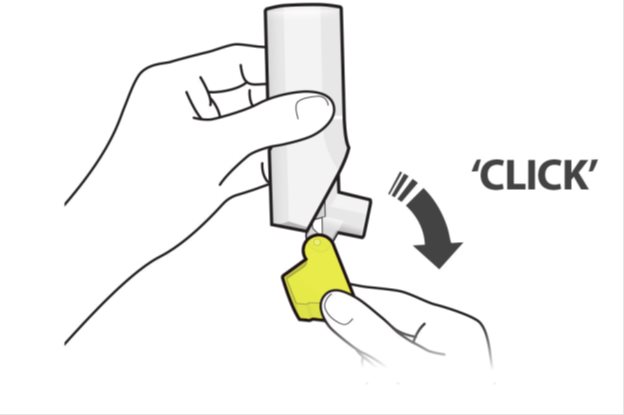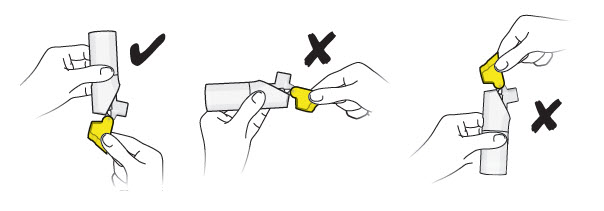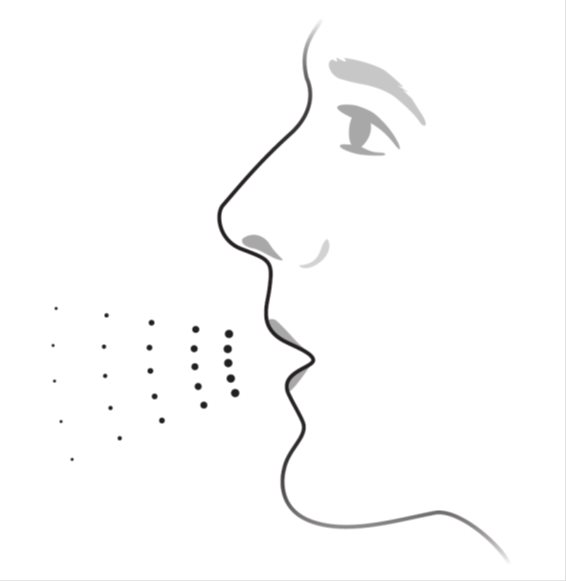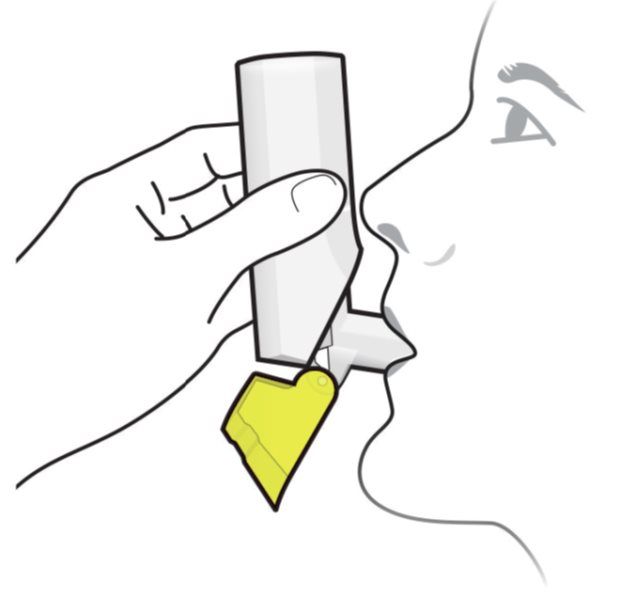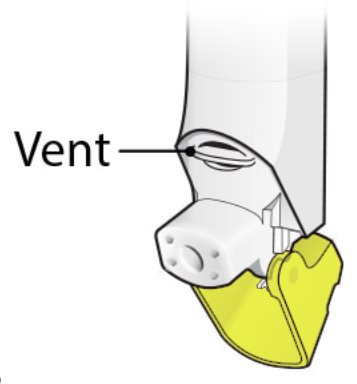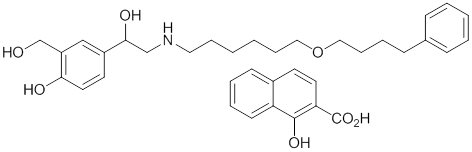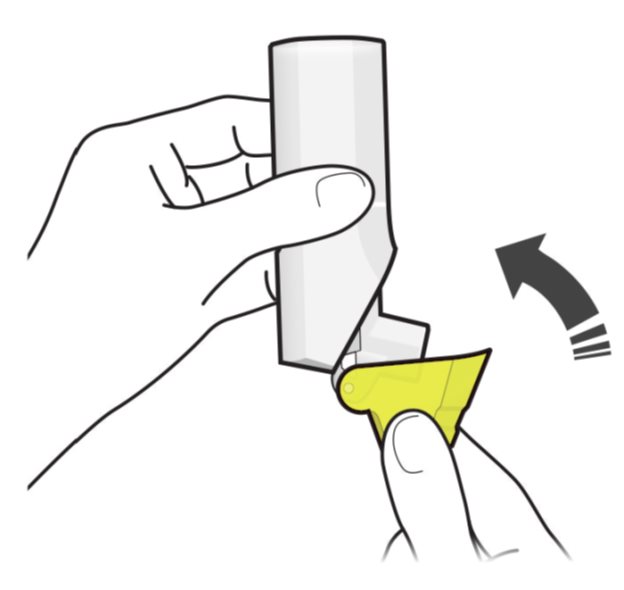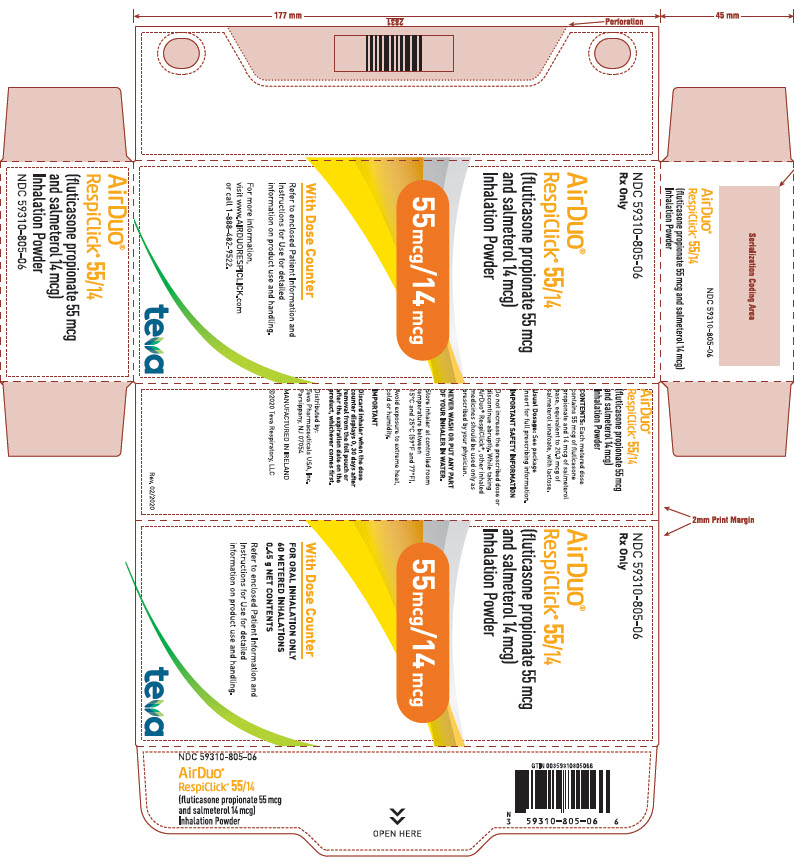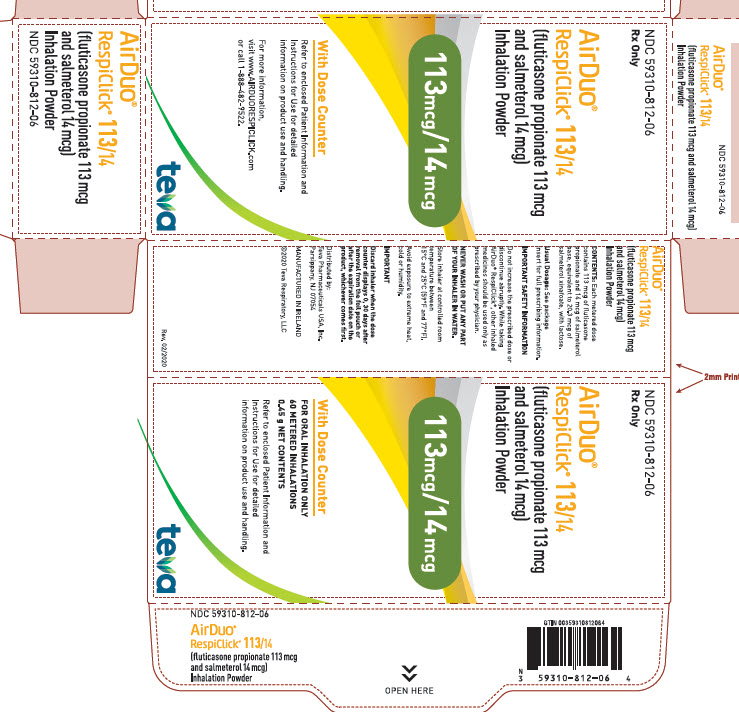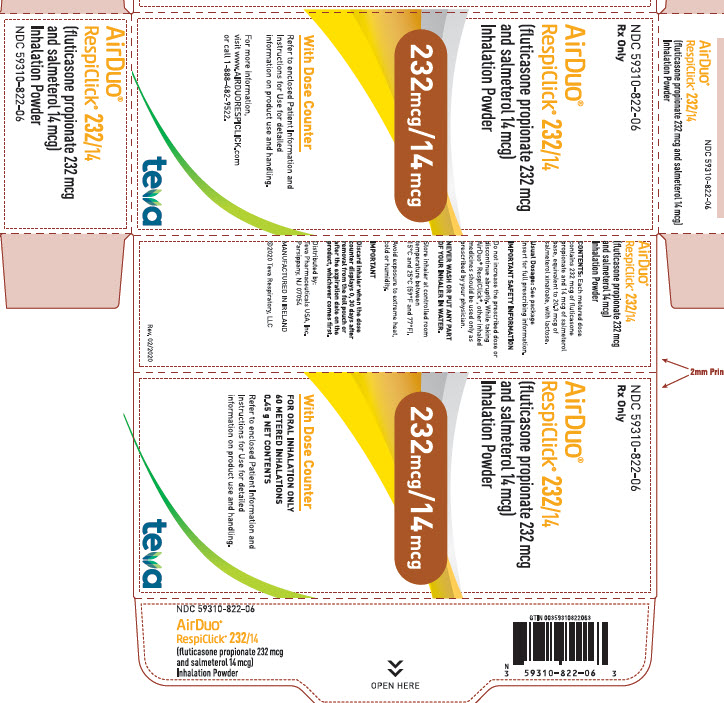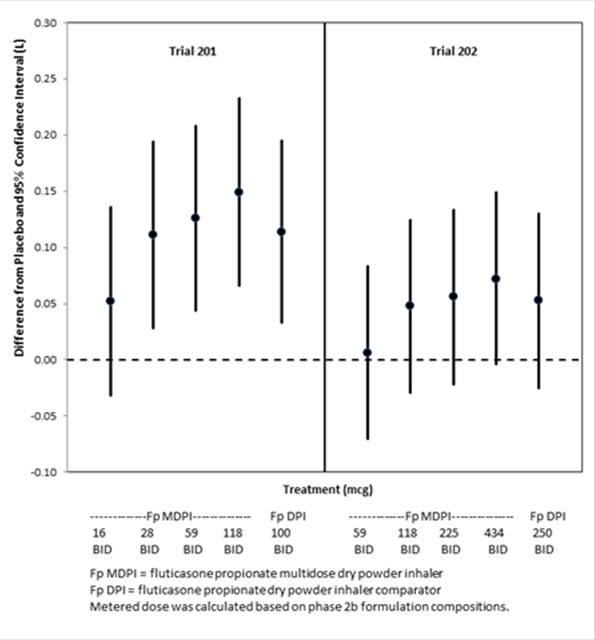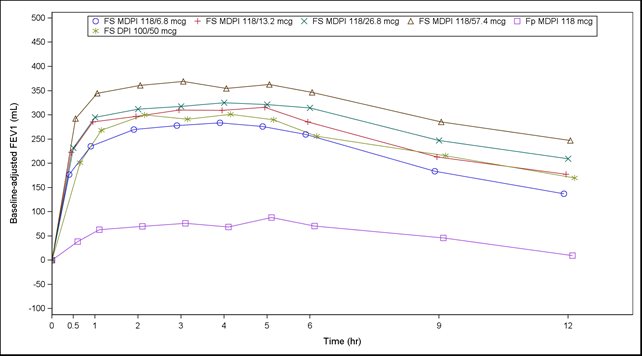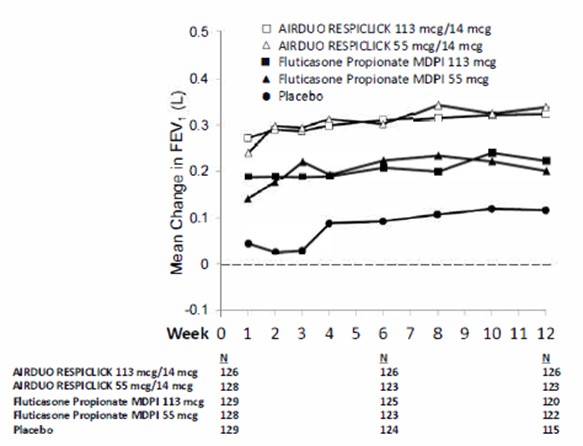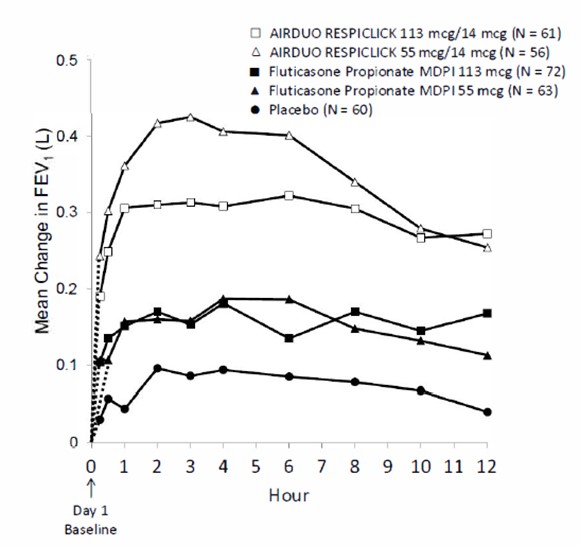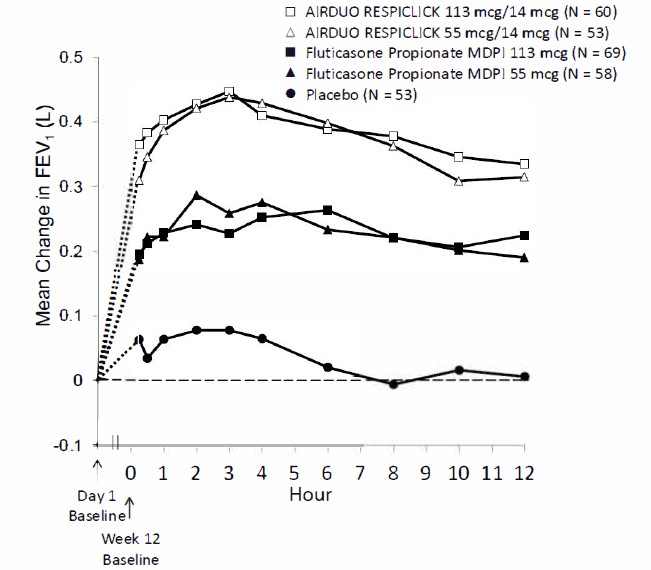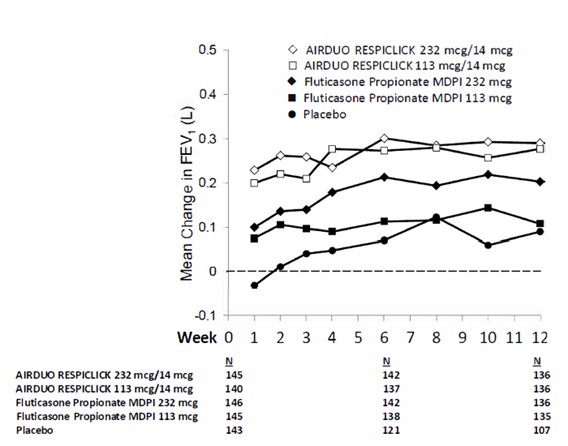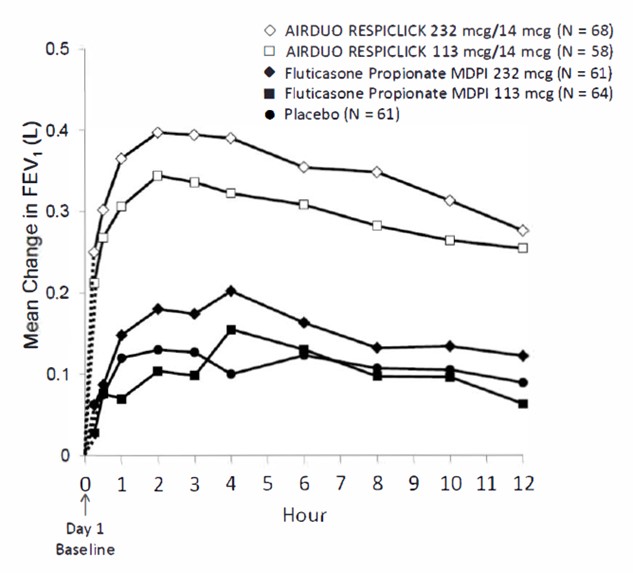 DRUG LABEL: AirDuo RespiClick
NDC: 59310-805 | Form: POWDER, METERED
Manufacturer: Teva Respiratory, LLC
Category: prescription | Type: HUMAN PRESCRIPTION DRUG LABEL
Date: 20240206

ACTIVE INGREDIENTS: FLUTICASONE PROPIONATE 55 ug/1 1; SALMETEROL XINAFOATE 14 ug/1 1
INACTIVE INGREDIENTS: LACTOSE MONOHYDRATE

HIGHLIGHTS OF PRESCRIBING INFORMATION

These highlights do not include all the information needed to use AIRDUO® RESPICLICK® safely and effectively. See full prescribing information for AIRDUO RESPICLICK.
AIRDUO RESPICLICK (fluticasone propionate and salmeterol) inhalation powder, for oral inhalation use
Initial U.S. Approval: 2000

1 INDICATIONS AND USAGE

AIRDUO RESPICLICK is a combination of fluticasone propionate, a corticosteroid, and salmeterol, a long-acting beta2-adrenergic agonist (LABA), indicated for treatment of asthma in adult and pediatric patients aged 12 years and older. AIRDUO RESPICLICK should be used for patients not adequately controlled on a long term asthma control medication such as an inhaled corticosteroid or whose disease warrants initiation of treatment with both an inhaled corticosteroid and long acting beta2-adrenergic agonist (LABA). (1)

Limitations of Use: Not indicated for the relief of acute bronchospasm. (1)

2 DOSAGE AND ADMINISTRATION

For oral inhalation only. (2.1)

- Starting dosage is based on prior asthma therapy and disease severity. (2.2)
- 1 inhalation of AIRDUO RESPICLICK 55 mcg/14 mcg, 113 mcg/14 mcg or 232 mcg/14 mcg twice daily. (2.2)
- Do not use with a spacer or volume holding chamber. (2.2)

3 DOSAGE FORMS AND STRENGTHS

Inhalation powder: 55 mcg/14 mcg, 113 mcg/14 mcg, or 232 mcg/14 mcg of fluticasone propionate/salmeterol in each actuation. (3)

4 CONTRAINDICATIONS

- Primary treatment of status asthmaticus or acute episodes of asthma requiring intensive measures. (4)
- Severe hypersensitivity to milk proteins or any ingredients of AIRDUO RESPICLICK. (4)

5 WARNINGS AND PRECAUTIONS

- LABA monotherapy increases the risk of serious asthma-related events. (5.1)
- Deterioration of asthma and acute episodes: Do not use for relief of acute symptoms. Patients require immediate re-evaluation during rapidly deteriorating asthma. (5.2)
- Do not use in combination with an additional medicine containing LABA because of risk of overdose. (5.3)
- Localized infections: Candida albicans infection of the mouth and pharynx may occur. Monitor patients periodically. Advise the patient to rinse his/her mouth with water without swallowing after inhalation to help reduce the risk. (5.4)
- Immunosuppression: Potential worsening of existing tuberculosis, fungal, bacterial, viral, parasitic infection, or ocular herpes simplex. Use with caution in patients with these infections. More serious or even fatal course of chickenpox or measles can occur in susceptible patients. (5.5)
- Transferring patients from systemic corticosteroids: Risk of impaired adrenal function when transferring from systemic corticosteroids. Taper patients slowly from systemic corticosteroids if transferring to AIRDUO RESPICLICK. (5.6)
- Hypercorticism and adrenal suppression: May occur with very high dosages or at the regular dosage in susceptible individuals. If such changes occur, discontinue AIRDUO RESPICLICK slowly. (5.7)
- Paradoxical bronchospasm: Discontinue AIRDUO RESPICLICK and institute alternative therapy if paradoxical bronchospasm occurs. (5.9)
- Use with caution in patients with cardiovascular or central nervous system disorders because of beta adrenergic stimulation. (5.11)
- Decreases in bone mineral density: Monitor patients with major risk factors for decreased bone mineral content. (5.12)
- Monitor growth of pediatric patients. (5.13)
- Close monitoring for glaucoma and cataracts is warranted. (5.14)
- Be alert to eosinophilic conditions, hypokalemia, and hyperglycemia. (5.15, 5.17)
- Use with caution in patients with convulsive disorders, thyrotoxicosis, diabetes mellitus, and ketoacidosis. (5.16)

6 ADVERSE REACTIONS

Most common adverse reactions (greater than or equal to 3%): nasopharyngitis, oral candidiasis, headache, cough and back pain. (6.1)

To report SUSPECTED ADVERSE REACTIONS, contact Teva Pharmaceuticals at 1-888-483-8279 or FDA at 1-800-FDA-1088 or www.fda.gov/medwatch.

7 DRUG INTERACTIONS

- Avoid strong cytochrome P450 3A4 inhibitors (e.g., ritonavir, ketoconazole): May increase risk of systemic corticosteroid and cardiovascular effects. (7.1)
- Monoamine oxidase inhibitors and tricyclic antidepressants: Use with extreme caution. May potentiate effect of salmeterol on vascular system. (7.2)
- Beta‑blockers: Use with caution. May block bronchodilatory effects of beta‑agonists and produce severe bronchospasm. (7.3)
- Diuretics: Use with caution. Electrocardiographic changes and/or hypokalemia associated with non‑potassium‑sparing diuretics may worsen with concomitant beta‑agonists. (7.4)

8 USE IN SPECIFIC POPULATIONS

Hepatic impairment: Monitor for systemic corticosteroid effects. (8.6)

FULL PRESCRIBING INFORMATION

1 INDICATIONS AND USAGE

AIRDUO® RESPICLICK® is indicated for the treatment of asthma in adult and pediatric patients aged 12 years and older. AIRDUO RESPICLICK should be used for patients not adequately controlled on a long term asthma control medication such as an inhaled corticosteroid or whose disease warrants initiation of treatment with both an inhaled corticosteroid and long acting beta2-adrenergic agonist (LABA).

Limitations of Use:

AIRDUO RESPICLICK is not indicated for the relief of acute bronchospasm.

2 DOSAGE AND ADMINISTRATION

2.1 Administration Instructions

- AIRDUO RESPICLICK is for oral inhalation and does not require priming.
- Do not use AIRDUO RESPICLICK with a spacer or volume holding chamber.
- Do not use more than two times every 24 hours. More frequent administration or a greater number of daily inhalations (more than one inhalation twice daily) is not recommended as some patients are more likely to experience adverse reactions with higher salmeterol dosages.
- Avoid the concomitant use of other long acting beta2-adrenergic agonist (LABAs) [see Warnings and Precautions (5.3, 5.11)].
- If asthma symptoms arise in the period between doses, an inhaled, short-acting beta2-agonist should be taken for immediate relief.

2.2 Recommended Dosage

Administer 1 inhalation of AIRDUO RESPICLICK twice daily by oral inhalation (approximately 12 hours apart at the same time every day). Rinse the mouth with water without swallowing after each inhalation.

Dosage Selection

The recommended starting dosage for AIRDUO RESPICLICK is based on asthma severity and current inhaled corticosteroid use and strength.

- Patients not taking inhaled corticosteroids (ICS) (with less severe asthma):
  - 1 inhalation of 55 mcg/14 mcg AIRDUO RESPICLICK dose strength (55 mcg of fluticasone propionate and 14 mcg of salmeterol), twice daily by oral inhalation.
- Patients with greater asthma severity, use the higher dose strengths:
  - 1 inhalation of 113 mcg/14 mcg AIRDUO RESPICLICK (113 mcg of fluticasone propionate and 14 mcg of salmeterol) twice daily; or
  - 1 inhalation of 232 mcg/14 mcg AIRDUO RESPICLICK (232 mcg of fluticasone propionate and 14 mcg of salmeterol) twice daily
- Patients switching to AIRDUO RESPICLICK from another inhaled corticosteroid or combination product:
  - 1 inhalation of low (55 mcg/14 mcg), medium (113 mcg/14 mcg) or high (232 mcg/14 mcg) AIRDUO RESPICLICK twice daily by oral inhalation based on the strength of the previous inhaled corticosteroid product, or the strength of the inhaled corticosteroid from a combination product, and disease severity.
- The maximum recommended dosage of AIRDUO RESPICLICK is 232 mcg/14 mcg twice daily.

General Dosing Information

Improvement in asthma control following AIRDUO RESPICLICK administration can occur within 15 minutes of beginning treatment; although maximum benefit may not be achieved for 1 week or longer after starting treatment. Individual patients will experience a variable time to onset and degree of symptom relief. For patients who do not respond adequately to the starting dose of AIRDUO RESPICLICK after 2 weeks of therapy, consider increasing the strength (replace with higher strength) to possibly provide additional improvement in asthma control.

If a previously effective dosage regimen fails to provide adequate improvement in asthma control, re-evaluate the therapeutic regimen, including patient compliance and inhaler technique, and consider additional therapeutic options (e.g., increasing the dose of AIRDUO RESPICLICK with a higher strength, adding additional controller therapies). After asthma stability has been achieved, it is desirable to titrate to the lowest effective dosage to reduce the risk of adverse reactions.

2.3 Storing and Cleaning the Inhaler

- Keep the inhaler in a cool dry place.
- Routine maintenance is not required. If the mouthpiece needs cleaning, gently wipe the mouthpiece with a dry cloth or tissue as needed.
- Never wash or put any part of the inhaler in water.

2.4 Dose Counter

The AIRDUO RESPICLICK inhaler has a dose counter:

- The number 60 is displayed (prior to use).
- The dose counter will count down each time the mouthpiece is opened and closed [see Patient Counseling Information (17)].

3 DOSAGE FORMS AND STRENGTHS

Inhalation powder: an inhalation-driven, multidose dry powder inhaler (MDPI) for oral inhalation that meters 55 mcg, 113 mcg, or 232 mcg of fluticasone propionate with 14 mcg of salmeterol from the device reservoir and delivers 49 mcg, 100 mcg, or 202 mcg of fluticasone propionate with 12.75 mcg of salmeterol, respectively, from the mouthpiece per actuation. The AIRDUO RESPICLICK is a white inhaler with a yellow cap, and is provided in a sealed foil pouch with desiccant [see How Supplied/Storage and Handling (16)].

4 CONTRAINDICATIONS

AIRDUO RESPICLICK is contraindicated in:

- the primary treatment of status asthmaticus or other acute episodes of asthma where intensive measures are required [see Warnings and Precautions (5.2)].
- patients with known severe hypersensitivity to milk proteins or who have demonstrated hypersensitivity to fluticasone propionate or any of the excipients [see Warnings and Precautions (5.10) and Description (11)].

5 WARNINGS AND PRECAUTIONS

5.1 Serious Asthma-Related Events – Hospitalizations, Intubations, Death

Use of LABA as monotherapy [without inhaled corticosteroids (ICS)] for asthma is associated with an increased risk of asthma-related death [see Salmeterol Multicenter Asthma Research Trial (SMART)]. Available data from controlled clinical trials also suggest that use of LABA as monotherapy increases the risk of asthma-related hospitalization in pediatric and adolescent patients. These findings are considered a class effect of LABA monotherapy. When LABA are used in fixed-dose combination with ICS, data from large clinical trials do not show a significant increase in the risk of serious asthma-related events (hospitalizations, intubations, death) compared with ICS alone [see Serious Asthma-Related Events with Inhaled Corticosteroid/Long-acting Beta2-adrenergic Agonists].

Serious Asthma-Related Events with Inhaled Corticosteroid/Long-acting Beta2-adrenergic Agonists

Four large, 26-week, randomized, blinded, active-controlled clinical safety trials were conducted to evaluate the risk of serious asthma-related events when LABA were used in fixed-dose combination with ICS compared with ICS alone in subjects with asthma. Three (3) trials included adult and adolescent subjects aged 12 years and older: 1 trial compared budesonide/formoterol to budesonide, 1 trial compared fluticasone propionate/salmeterol inhalation powder to fluticasone propionate inhalation powder, and 1 trial compared mometasone furoate/formoterol to mometasone furoate. The fourth trial included pediatric subjects aged 4 to 11 years and compared fluticasone propionate/salmeterol inhalation powder to fluticasone propionate inhalation powder. The primary safety endpoint for all 4 trials was serious asthma-related events (hospitalizations, intubations, death). A blinded adjudication committee determined whether events were asthma-related.

The 3 adult and adolescent trials were designed to rule out a risk margin of 2.0, and the pediatric trial was designed to rule out a risk margin of 2.7. Each individual trial met its pre-specified objective and demonstrated non-inferiority of ICS/LABA to ICS alone. A meta-analysis of the 3 adult and adolescent trials did not show a significant increase in risk of a serious asthma-related event with ICS/LABA fixed-dose combination compared with ICS alone (Table 1). These trials were not designed to rule out all risk for serious asthma-related events with ICS/LABA compared with ICS.

Table 1. Meta-analysis of Serious Asthma-Related Events in Subjects with Asthma Aged 12 Years and Older

 | ICS/LABA; (n =17,537) a | ICS; (n = 17,552) a | ICS/LABA vs.; ICS; Hazard Ratio (95% CI)b
Serious asthma-related event c | 116 | 105 | 1.10 (0.85, 1.44)
Asthma-related death | 2 | 0
Asthma-related intubation (endotracheal) | 1 | 2
Asthma-related hospitalization (≥24-hour stay) | 115 | 105

ICS = Inhaled Corticosteroid; LABA = Long-acting Beta2-adrenergic Agonist.

a Randomized subjects who had taken at least 1 dose of study drug. Planned treatment used for analysis.

b Estimated using a Cox proportional hazards model for time to first event with baseline hazards stratified by each of the 3 trials.

c Number of subjects with events that occurred within 6 months after the first use of study drug or 7 days after the last date of study drug, whichever date was later. Subjects can have one or more events, but only the first event was counted for analysis. A single, blinded, independent adjudication committee determined whether events were asthma related.

The pediatric safety trial included 6,208 pediatric patients aged 4 to 11 years who received ICS/LABA (fluticasone propionate/salmeterol inhalation powder) or ICS (fluticasone propionate inhalation powder). In this trial 27/3,107 (0.9%) of patients treated with ICS/LABA and 21/3,101 (0.7%) of patients treated with ICS experienced a serious asthma‑related event. There were no asthma-related deaths or intubations. ICS/LABA did not show a significantly increased risk of a serious asthma-related event compared to ICS based on the prespecified risk margin (2.7), with an estimated hazard ratio of time to first event of 1.29 (95% CI: 0.73, 2.27).

Salmeterol Multicenter Asthma Research Trial (SMART)

A 28-week, placebo-controlled, U.S. trial that compared the safety of salmeterol with placebo, each added to usual asthma therapy, showed an increase in asthma-related deaths in subjects receiving salmeterol (13/13,176 in subjects treated with salmeterol versus 3/13,179 in subjects treated with placebo; relative risk: 4.37 [95% CI: 1.25, 15.34]). Use of background ICS was not required in SMART. The increased risk of asthma‑related death is considered a class effect of LABA monotherapy.

5.2 Deterioration of Disease and Acute Episodes

AIRDUO RESPICLICK should not be initiated in patients during rapidly deteriorating or potentially life‑threatening episodes of asthma. AIRDUO RESPICLICK has not been studied in subjects with acutely deteriorating asthma. The initiation of AIRDUO RESPICLICK in this setting is not appropriate.

Serious acute respiratory events, including fatalities, have been reported when salmeterol, a component of AIRDUO RESPICLICK, has been initiated in patients with significantly worsening or acutely deteriorating asthma. In most cases, these have occurred in patients with severe asthma (e.g., patients with a history of corticosteroid dependence, low pulmonary function, intubation, mechanical ventilation, frequent hospitalizations, previous life‑threatening acute asthma exacerbations) and in some patients with acutely deteriorating asthma (e.g., patients with significantly increasing symptoms; increasing need for inhaled, short‑acting beta2‑agonists; decreasing response to usual medications; increasing need for systemic corticosteroids; recent emergency room visits; deteriorating lung function). However, these events have occurred in a few patients with less severe asthma as well. It was not possible from these reports to determine whether salmeterol contributed to these events.

Increasing use of inhaled, short‑acting beta2‑agonists is a marker of deteriorating asthma. In this situation, the patient requires immediate reevaluation with reassessment of the treatment regimen, giving special consideration to the possible need for replacing the current strength of AIRDUO RESPICLICK with a higher strength, adding additional inhaled corticosteroid, or initiating systemic corticosteroids. Patients should not use more than 1 inhalation twice daily of AIRDUO RESPICLICK.

AIRDUO RESPICLICK should not be used for the relief of acute symptoms, i.e., as rescue therapy for the treatment of acute episodes of bronchospasm. An inhaled, short‑acting beta2‑agonist, not AIRDUO RESPICLICK, should be used to relieve acute symptoms such as shortness of breath. When prescribing AIRDUO RESPICLICK, the healthcare provider should also prescribe an inhaled, short‑acting beta2-agonist (e.g., albuterol) for treatment of acute symptoms, despite regular twice‑daily use of AIRDUO RESPICLICK.

When beginning treatment with AIRDUO RESPICLICK, patients who have been taking oral or inhaled, short‑acting beta2‑agonists on a regular basis (e.g., 4 times a day) should be instructed to discontinue the regular use of these drugs.

5.3 Avoid Excessive Use of AIRDUO RESPICLICK and Avoid Use with Other Long-Acting Beta2-Agonists

AIRDUO RESPICLICK should not be used more often than recommended, at higher doses than recommended, or in conjunction with other medicines containing LABA, as an overdose may result. Clinically significant cardiovascular effects and fatalities have been reported in association with excessive use of inhaled sympathomimetic drugs. Patients using AIRDUO RESPICLICK should not use another medicine containing a LABA (e.g., salmeterol, formoterol fumarate, arformoterol tartrate, indacaterol) for any reason.

5.4 Oropharyngeal Candidiasis

In clinical trials, the development of localized infections of the mouth and pharynx with Candida albicans has occurred in subjects treated with AIRDUO RESPICLICK. When such an infection develops, it should be treated with appropriate local or systemic (i.e., oral) antifungal therapy while treatment with AIRDUO RESPICLICK continues, but at times therapy with AIRDUO RESPICLICK may need to be interrupted. Advise the patient to rinse his/her mouth with water without swallowing following inhalation to help reduce the risk of oropharyngeal candidiasis.

5.5 Immunosuppression and Risk of Infections

Persons who are using drugs that suppress the immune system are more susceptible to infections than healthy individuals. Chickenpox and measles, for example, can have a more serious or even fatal course in susceptible adolescents or adults using corticosteroids. In such patients who have not had these diseases or who have not been properly immunized, particular care should be taken to avoid exposure. How the dose, route and duration of corticosteroid administration affect the risk of developing a disseminated infection is not known. The contribution of the underlying disease and/or prior corticosteroid treatment to the risk is also not known. If a patient is exposed to chickenpox, prophylaxis with varicella-zoster immune globulin (VZIG) or pooled intravenous immunoglobulin (IVIG) may be indicated. If a patient is exposed to measles, prophylaxis with pooled intramuscular immunoglobulin (IG) may be indicated. (See the respective package inserts for complete VZIG and IG prescribing information.) If chickenpox develops, treatment with antiviral agents may be considered.

Inhaled corticosteroids should be used with caution, if at all, in patients with active or quiescent tuberculosis infections of the respiratory tract; systemic fungal, bacterial, viral, or parasitic infections; or ocular herpes simplex.

5.6 Transferring Patients from Systemic Corticosteroid Therapy

HPA Suppression/Adrenal Insufficiency

Particular care is needed for patients who are transferred from systemically active corticosteroids to inhaled corticosteroids because deaths due to adrenal insufficiency have occurred in patients with asthma during and after transfer from systemic corticosteroids to less systemically available inhaled corticosteroids. After withdrawal from systemic corticosteroids, a number of months are required for recovery of hypothalamic‑pituitary‑adrenal (HPA) function.

Patients who have been previously maintained on 20 mg or more of prednisone (or its equivalent) may be most susceptible, particularly when their systemic corticosteroids have been almost completely withdrawn. During this period of HPA suppression, patients may exhibit signs and symptoms of adrenal insufficiency when exposed to trauma, surgery, or infection (particularly gastroenteritis) or other conditions associated with severe electrolyte loss. Although AIRDUO RESPICLICK may improve control of asthma symptoms during these episodes, in recommended doses it supplies less than normal physiological amounts of corticosteroid systemically and does NOT provide the mineralocorticoid activity that is necessary for coping with these emergencies.

During periods of stress or a severe asthmatic attack, patients who have been withdrawn from systemic corticosteroids should be instructed to resume oral corticosteroids (in large doses) immediately and to contact their physician for further instruction. These patients should also be instructed to carry a medical identification warning card indicating that they may need supplementary systemic corticosteroids during periods of stress or a severe asthma attack.

Patients requiring systemic corticosteroids should be weaned slowly from systemic corticosteroid use after transferring to AIRDUO RESPICLICK. Lung function (mean forced expiratory volume in 1 second [FEV1] or morning peak expiratory flow [AM PEF]), beta‑agonist use, and asthma symptoms should be carefully monitored during withdrawal of systemic corticosteroids. In addition to monitoring asthma signs and symptoms, patients should be observed for signs and symptoms of adrenal insufficiency, such as fatigue, lassitude, weakness, nausea and vomiting, and hypotension.

Unmasking of Allergic Conditions Previously Suppressed by Systemic Corticosteroids

Transfer of patients from systemic corticosteroid therapy to AIRDUO RESPICLICK may unmask allergic conditions previously suppressed by the systemic corticosteroid therapy (e.g., rhinitis, conjunctivitis, eczema, arthritis, eosinophilic conditions).

Corticosteroid Withdrawal Symptoms

During withdrawal from oral corticosteroids, some patients may experience symptoms of systemically active corticosteroid withdrawal (e.g., joint and/or muscular pain, lassitude, depression) despite maintenance or even improvement of respiratory function.

5.7 Hypercorticism and Adrenal Suppression

Fluticasone propionate, a component of AIRDUO RESPICLICK, will often help control asthma symptoms with less suppression of HPA function than therapeutically equivalent oral doses of prednisone. Since fluticasone propionate is absorbed into the circulation and can be systemically active at higher doses, the beneficial effects of AIRDUO RESPICLICK in minimizing HPA dysfunction may be expected only when recommended dosages are not exceeded and individual patients are titrated to the lowest effective dose. A relationship between plasma levels of fluticasone propionate and inhibitory effects on stimulated cortisol production has been shown after 4 weeks of treatment with fluticasone propionate inhalation aerosol. Since individual sensitivity to effects on cortisol production exists, physicians should consider this information when prescribing AIRDUO RESPICLICK.

Because of the possibility of significant systemic absorption of inhaled corticosteroids, patients treated with AIRDUO RESPICLICK should be observed carefully for any evidence of systemic corticosteroid effects. Particular care should be taken in observing patients postoperatively or during periods of stress for evidence of inadequate adrenal response.

It is possible that systemic corticosteroid effects such as hypercorticism and adrenal suppression (including adrenal crisis) may appear in a small number of patients who are sensitive to these effects. If such effects occur, AIRDUO RESPICLICK should be reduced slowly, consistent with accepted procedures for reducing systemic corticosteroids, and for management of asthma symptoms.

5.8 Drug Interactions with Strong Cytochrome P450 3A4 Inhibitors

The use of strong cytochrome P450 3A4 (CYP3A4) inhibitors (e.g., ritonavir, atazanavir, clarithromycin, indinavir, itraconazole, nefazodone, nelfinavir, saquinavir, ketoconazole, telithromycin) with AIRDUO RESPICLICK is not recommended because increased systemic corticosteroid and increased cardiovascular adverse effects may occur [see Drug Interactions (7.1) and Clinical Pharmacology (12.3)].

5.9 Paradoxical Bronchospasm and Upper Airway Symptoms

As with other inhaled medicines, AIRDUO RESPICLICK can produce paradoxical bronchospasm, which may be life‑threatening. If paradoxical bronchospasm occurs following dosing with inhaled fluticasone propionate/salmeterol medicines, it should be treated immediately with an inhaled, short-acting bronchodilator; inhaled fluticasone propionate/salmeterol medicines should be discontinued immediately; and alternative therapy should be instituted. Upper airway symptoms of laryngeal spasm, irritation, or swelling, such as stridor and choking, have been reported in patients receiving inhaled fluticasone propionate/salmeterol medicines.

5.10 Hypersensitivity Reactions, Including Anaphylaxis

Immediate hypersensitivity reactions (e.g., urticaria, angioedema, rash, bronchospasm, hypotension), including anaphylaxis, may occur after administration of AIRDUO RESPICLICK. There have been reports of anaphylactic reactions in patients with severe milk protein allergy after inhalation of other powder products containing lactose; therefore, patients with severe milk protein allergy should not use AIRDUO RESPICLICK [see Contraindications (4)].

5.11 Cardiovascular and Central Nervous System Effects

Excessive beta‑adrenergic stimulation has been associated with seizures, angina, hypertension or hypotension, tachycardia with rates up to 200 beats/min, arrhythmias, nervousness, headache, tremor, palpitation, nausea, dizziness, fatigue, malaise, and insomnia [see Overdosage (10)]. Therefore, AIRDUO RESPICLICK, like all products containing sympathomimetic amines, should be used with caution in patients with cardiovascular disorders, especially coronary insufficiency, cardiac arrhythmias, and hypertension.

Salmeterol, a component of AIRDUO RESPICLICK, can produce a clinically significant cardiovascular effect in some patients as measured by pulse rate, blood pressure, and/or symptoms. Although such effects are uncommon after administration of salmeterol at recommended doses, if they occur, the drug may need to be discontinued. In addition, beta‑agonists have been reported to produce electrocardiogram (ECG) changes, such as flattening of the T wave, prolongation of the QTc interval, and ST segment depression. The clinical significance of these findings is unknown. Large doses of inhaled or oral salmeterol (12 to 20 times the recommended dose) have been associated with clinically significant prolongation of the QTc interval, which has the potential for producing ventricular arrhythmias. Fatalities have been reported in association with excessive use of inhaled sympathomimetic drugs.

5.12 Reduction in Bone Mineral Density

Decreases in bone mineral density (BMD) have been observed with long‑term administration of products containing inhaled corticosteroids. The clinical significance of small changes in BMD with regard to long‑term consequences such as fracture is unknown. Patients with major risk factors for decreased bone mineral content, such as prolonged immobilization, family history of osteoporosis, or chronic use of drugs that can reduce bone mass (e.g., anticonvulsants, oral corticosteroids) should be monitored and treated with established standards of care.

5.13 Effect on Growth

Orally inhaled corticosteroids, including AIRDUO RESPICLICK, may cause a reduction in growth velocity when administered to pediatric patients. Monitor the growth of pediatric patients receiving AIRDUO RESPICLICK routinely (e.g., via stadiometry). To minimize the systemic effects of orally inhaled corticosteroids, including AIRDUO RESPICLICK, titrate each patient’s dosage to the lowest dosage that effectively controls his/her symptoms [see Dosage and Administration (2), Use in Specific Populations (8.4)].

5.14 Glaucoma and Cataracts

Glaucoma, increased intraocular pressure, and cataracts have been reported in patients following the long-term administration of inhaled corticosteroids, including fluticasone propionate, a component of AIRDUO RESPICLICK. Therefore, close monitoring is warranted in patients with a change in vision or with a history of increased intraocular pressure, glaucoma, and/or cataracts.

Effects of treatment with other Fluticasone Propionate and Salmeterol Inhalation Powder 500 mcg/50 mcg, fluticasone propionate 500 mcg, salmeterol 50 mcg, or placebo on development of cataracts or glaucoma was evaluated in a subset of 658 subjects with COPD in the 3-year survival trial. Ophthalmic examinations were conducted at baseline and at 48, 108, and 158 weeks. Conclusions about cataracts cannot be drawn from this trial because the high incidence of cataracts at baseline (61% to 71%) resulted in an inadequate number of subjects treated with other Fluticasone Propionate and Salmeterol Inhalation Powder 500 mcg/50 mcg who were eligible and available for evaluation of cataracts at the end of the trial (n = 53). The incidence of newly diagnosed glaucoma was 2% with other Fluticasone Propionate and Salmeterol Inhalation Powder 500 mcg/50 mcg, 5% with fluticasone propionate, 0% with salmeterol, and 2% with placebo.

5.15 Eosinophilic Conditions and Churg-Strauss Syndrome

In rare cases, patients on inhaled fluticasone propionate, a component of AIRDUO RESPICLICK, may present with systemic eosinophilic conditions. Some of these patients have clinical features of vasculitis consistent with Churg‑Strauss syndrome, a condition that is often treated with systemic corticosteroid therapy. These events usually, but not always, have been associated with the reduction and/or withdrawal of oral corticosteroid therapy following the introduction of fluticasone propionate. Cases of serious eosinophilic conditions have also been reported with other inhaled corticosteroids in this clinical setting. Physicians should be alert to eosinophilia, vasculitic rash, worsening pulmonary symptoms, cardiac complications, and/or neuropathy presenting in their patients. A causal relationship between fluticasone propionate and these underlying conditions has not been established.

5.16 Coexisting Conditions

AIRDUO RESPICLICK, like all medicines containing sympathomimetic amines, should be used with caution in patients with convulsive disorders or thyrotoxicosis and in those who are unusually responsive to sympathomimetic amines. Doses of the related beta2‑adrenoceptor agonist albuterol, when administered intravenously, have been reported to aggravate preexisting diabetes mellitus and ketoacidosis.

5.17 Hypokalemia and Hyperglycemia

Beta‑adrenergic agonist medicines may produce significant hypokalemia in some patients, possibly through intracellular shunting, which has the potential to produce adverse cardiovascular effects [see Clinical Pharmacology (12.2)]. The decrease in serum potassium is usually transient, not requiring supplementation. Clinically significant changes in blood glucose and/or serum potassium were seen infrequently during clinical trials with AIRDUO RESPICLICK at recommended doses.

6 ADVERSE REACTIONS

The following clinically significant adverse reactions are described elsewhere in the labeling:

- Serious asthma-related events – hospitalizations, intubations, death [see Warnings and Precautions (5.1)]
- Oropharyngeal candidiasis [see Warnings and Precautions (5.4)]
- Immunosuppression and risk of infections [see Warnings and Precautions (5.5)]
- Hypercorticism and adrenal suppression [see Warnings and Precautions (5.7)]
- Cardiovascular and central nervous system effects [see Warnings and Precautions (5.11)]
- Reduction in bone mineral density [see Warnings and Precautions (5.12)]
- Growth effects in pediatrics [see Warnings and Precautions (5.13)]
- Glaucoma and cataracts [see Warnings and Precautions (5.14)]

6.1 Clinical Trials Experience in Asthma

Because clinical trials are conducted under widely varying conditions, adverse reaction rates observed in the clinical trials of a drug cannot be directly compared to rates in the clinical trials of another drug and may not reflect the rates observed in practice.

In two placebo-controlled, 12-week, clinical studies (Trials 1 and 2) [see Clinical Studies (14)], a total of 1,364 adolescent and adult patients with persistent symptomatic asthma despite ICS or ICS/LABA therapy were treated twice daily with either placebo; fluticasone propionate MDPI 55 mcg, 113 mcg, or 232 mcg (ARMONAIR RESPICLICK, hereafter referred to as fluticasone propionate MDPI); or AIRDUO RESPICLICK 55 mcg/14 mcg, 113 mcg/14 mcg, or 232 mcg/14 mcg. Sixty percent of patients were female and 80% of patients were white. The average duration of exposure was 82 to 84 days in the fluticasone propionate MDPI and AIRDUO RESPICLICK treatment groups compared with 75 days in the placebo group. Table 2 displays the incidence of most common adverse reactions in pooled Trials 1 and 2.

Table 2: Adverse Reactions with ≥3% Incidence with AIRDUO RESPICLICK, and More Common than Placebo in Subjects with Asthma (Trials 1 and 2)

Adverse Reaction | Fluticasone Propionate MDPI55 mcg (n=129)% | Fluticasone Propionate MDPI113 mcg (n=274)% | Fluticasone Propionate MDPI232 mcg (n=146)% | AIRDUO RESPICLICK 55 mcg/14 mcg (n=128)% | AIRDUO RESPICLICK 113 mcg/14 mcg (n=269)% | AIRDUO RESPICLICK 232 mcg/14 mcg (n=145)% | Placebo (n=273)%
Nasopharyngitis | 5.4 | 5.8 | 4.8 | 8.6 | 4.8 | 6.9 | 4.4
Oral candidiasis* | 3.1 | 2.9 | 4.8 | 1.6 | 2.2 | 3.4 | 0.7
Headache | 1.6 | 7.3 | 4.8 | 5.5 | 4.8 | 2.8 | 4.4
Cough | 1.6 | 1.8 | 3.4 | 2.3 | 3.7 | 0.7 | 2.6
Back pain | 0 | 1.5 | 1.4 | 3.1 | 0.7 | 0 | 1.8

*Oral candidiasis includes oropharyngeal candidiasis, oral fungal infection, and oropharyngitis fungal

Other adverse reactions not previously listed (and occurring in <3% of patients and in three or more patients on AIRDUO RESPICLICK) that were reported more frequently by patients with asthma treated with AIRDUO RESPICLICK compared with patients treated with placebo include the following:

Sinusitis, oropharyngeal pain, pharyngitis, dizziness, influenza, rhinitis allergic, respiratory tract infection, rhinitis, nasal congestion, abdominal pain upper, myalgia, pain in extremity, dyspepsia, laceration, dermatitis contact, and palpitations.

Long Term Safety Study: This was a 26-week, open labeled study of 674 patients previously treated with ICS who were treated twice daily with fluticasone propionate MDPI 113 mcg or 232 mcg; AIRDUO RESPICLICK 113 mcg/14 mcg or 232 mcg/14 mcg; fluticasone propionate inhalation aerosol 110 mcg or 220 mcg; fluticasone propionate and salmeterol inhalation powder (250 mcg/50 mcg), or fluticasone propionate and salmeterol inhalation powder (500 mcg/50 mcg). The types of adverse reactions were similar to those reported above in placebo-controlled studies.

6.2 Postmarketing Experience

In addition to adverse reactions reported from clinical trials, the following adverse reactions have been identified during post approval use of fluticasone propionate and/or salmeterol regardless of indication. Because these reactions are reported voluntarily from a population of uncertain size, it is not always possible to reliably estimate their frequency or establish a causal relationship to drug exposure. These events have been chosen for inclusion due to either their seriousness, frequency of reporting, or causal connection to fluticasone propionate and/or salmeterol or a combination of these factors.

Cardiac Disorders: Arrhythmias (including atrial fibrillation, extrasystoles, supraventricular tachycardia), ventricular tachycardia.

Endocrine Disorders: Cushing’s syndrome, Cushingoid features, growth velocity reduction in children/adolescents, hypercorticism.

Eye Disorders: Glaucoma, blurred vision and central serous chorioretinopathy.

Gastrointestinal Disorders: Abdominal pain, dyspepsia, xerostomia.

Immune System Disorders: Immediate and delayed hypersensitivity reaction (including very rare anaphylactic reaction). Very rare anaphylactic reaction in patients with severe milk protein allergy.

Infections and Infestations: Esophageal candidiasis.

Metabolic and Nutrition Disorders: Hyperglycemia, weight gain.

Musculoskeletal, Connective Tissue, and Bone Disorders: Arthralgia, cramps, myositis, osteoporosis.

Nervous System Disorders: Paresthesia, restlessness.

Psychiatric Disorders: Agitation, aggression, depression. Behavioral changes, including hyperactivity and irritability, have been reported very rarely and primarily in children.

Reproductive System and Breast Disorders: Dysmenorrhea.

Respiratory, Thoracic, and Mediastinal Disorders: Chest congestion; chest tightness, dyspnea; facial and oropharyngeal edema, immediate bronchospasm; paradoxical bronchospasm; tracheitis; wheezing; reports of upper respiratory symptoms of laryngeal spasm, irritation, or swelling such as stridor or choking.

Skin and Subcutaneous Tissue Disorders: Ecchymoses, photodermatitis.

Vascular Disorders: Pallor.

7 DRUG INTERACTIONS

AIRDUO RESPICLICK has been used concomitantly with other drugs, including short‑acting beta2‑agonists, and intranasal corticosteroids, commonly used in patients with asthma without adverse drug reactions [see Clinical Pharmacology (12.2)]. No formal drug interaction trials have been performed with AIRDUO RESPICLICK.

7.1 Inhibitors of Cytochrome P450 3A4

Fluticasone propionate and salmeterol, the individual components of AIRDUO RESPICLICK, are substrates of CYP3A4. The use of strong CYP3A4 inhibitors (e.g., ritonavir, atazanavir, clarithromycin, indinavir, itraconazole, nefazodone, nelfinavir, saquinavir, ketoconazole, telithromycin) with AIRDUO RESPICLICK is not recommended because increased systemic corticosteroid and increased cardiovascular adverse effects may occur.

Ritonavir: Fluticasone Propionate: A drug interaction trial with fluticasone propionate aqueous nasal spray in healthy subjects has shown that ritonavir (a strong CYP3A4 inhibitor) can significantly increase plasma fluticasone propionate exposure, resulting in significantly reduced serum cortisol concentrations [see Clinical Pharmacology (12.3)]. During postmarketing use, there have been reports of clinically significant drug interactions in patients receiving fluticasone propionate and ritonavir, resulting in systemic corticosteroid effects including Cushing’s syndrome and adrenal suppression.

Ketoconazole: Fluticasone Propionate: Coadministration of orally inhaled fluticasone propionate (1,000 mcg) and ketoconazole (200 mg once daily) resulted in a 1.9‑fold increase in plasma fluticasone propionate exposure and a 45% decrease in plasma cortisol area under the curve (AUC) but had no effect on urinary excretion of cortisol.

Salmeterol: In a drug interaction trial in 20 healthy subjects, coadministration of inhaled salmeterol (50 mcg twice daily) and oral ketoconazole (400 mg once daily) for 7 days resulted in greater systemic exposure to salmeterol (AUC increased 16‑fold and Cmax increased 1.4‑fold). Three (3) subjects were withdrawn due to beta2‑agonist side effects (2 with prolonged QTc and 1 with palpitations and sinus tachycardia). Although there was no statistical effect on the mean QTc, coadministration of salmeterol and ketoconazole was associated with more frequent increases in QTc duration compared with salmeterol and placebo administration [see Clinical Pharmacology (12.3)].

7.2 Monoamine Oxidase Inhibitors and Tricyclic Antidepressants

AIRDUO RESPICLICK should be administered with extreme caution to patients being treated with monoamine oxidase inhibitors or tricyclic antidepressants, or within 2 weeks of discontinuation of such agents, because the action of salmeterol, a component of AIRDUO RESPICLICK, on the vascular system may be potentiated by these agents.

7.3 Beta-Adrenergic Receptor Blocking Agents

Beta‑blockers not only block the pulmonary effect of beta‑agonists, such as salmeterol, a component of AIRDUO RESPICLICK, but may also produce severe bronchospasm in patients with asthma. Therefore, patients with asthma should not normally be treated with beta‑blockers. However, under certain circumstances, there may be no acceptable alternatives to the use of beta‑adrenergic blocking agents for these patients; cardioselective beta‑blockers could be considered, although they should be administered with caution.

7.4 Non-Potassium-Sparing Diuretics

The ECG changes and/or hypokalemia that may result from the administration of non–potassium‑sparing diuretics (such as loop or thiazide diuretics) can be acutely worsened by beta‑agonists, such as salmeterol, a component of AIRDUO RESPICLICK, especially when the recommended dose of the beta‑agonist is exceeded. Although the clinical significance of these effects is not known, caution is advised in the coadministration of AIRDUO RESPICLICK with non–potassium‑sparing diuretics.

8 USE IN SPECIFIC POPULATIONS

8.1 Pregnancy

Risk Summary

There are no randomized clinical studies of AIRDUO RESPICLICK or individual monoproducts, fluticasone propionate and salmeterol, in pregnant women. There are clinical considerations with the use of AIRDUO RESPICLICK in pregnant women [see Clinical Considerations]. Animal reproduction studies are available with the combination of fluticasone propionate and salmeterol as well as individual components. In animals, teratogenicity characteristic of corticosteroids, decreased fetal body weight and/or skeletal variations, in rats, mice, and rabbits were observed with subcutaneously administered maternal toxic doses of fluticasone propionate less than the maximum recommended human daily inhaled dose (MRHDID) on a mcg/m^2 basis [see Data]. However, fluticasone propionate administered via inhalation to rats decreased fetal body weight, but did not induce teratogenicity at a maternal toxic dose less than the MRHDID on a mcg/m^2 basis [see Data]. Experience with oral corticosteroids suggests that rodents are more prone to teratogenic effects from corticosteroids than humans. Oral administration of salmeterol to pregnant rabbits caused teratogenicity characteristic of beta-adrenoceptor stimulation at maternal doses approximately 700 times the MRHDID on a mcg/m^2 basis. These adverse effects generally occurred at large multiples of the MRHDID when salmeterol was administered by the oral route to achieve high systemic exposures. No such effects occurred at an oral salmeterol dose approximately 420 times the MRHDID [see Data].

The estimated risk of major birth defects and miscarriage for the indicated population is unknown. In the U.S. general population, the estimated risk of major birth defects and miscarriage in clinically recognized pregnancies is 2% to 4% and 15% to 20%, respectively.

Clinical Considerations

Disease‑Associated Maternal and/or Embryo/Fetal Risk

In women with poorly or moderately controlled asthma, there is an increased risk of several perinatal adverse outcomes such as preeclampsia in the mother and prematurity, low birth weight, and small for gestational age in the neonate. Pregnant women with asthma should be closely monitored and medication adjusted as necessary to maintain optimal asthma control.

Data

Animal Data

Fluticasone Propionate and Salmeterol: In an embryo/fetal development study with pregnant rats that received the combination of subcutaneous administration of fluticasone propionate and oral administration of salmeterol at doses of 0/1000, 30/0, 10/100, 30/1000, and 100/10,000 mcg/kg/day (as fluticasone propionate/salmeterol) during the period of organogenesis, findings were generally consistent with the individual monoproducts and there was no exacerbation of expected fetal effects. Omphalocele, increased embryo/fetal deaths, decreased body weight, and skeletal variations were observed in rat fetuses, in the presence of maternal toxicity, when combining fluticasone propionate at a dose approximately 2 times the MRHDID (on a mcg/m^2 basis at a maternal subcutaneous dose of 100 mcg/kg/day) and a dose of salmeterol at approximately 3500 times the MRHDID (on a mcg/m^2 basis at a maternal oral dose of 10,000 mcg/kg/day). The rat no observed adverse effect level (NOAEL) was observed when combining fluticasone propionate at a dose 0.6 times the MRHDID (on a mcg/m^2 basis at a maternal subcutaneous dose of 30 mcg/kg/day) and a dose of salmeterol at approximately 350 times the MRHDID (on a mcg/m^2 basis at a maternal oral dose of 1000 mcg/kg/day).

In an embryo/fetal development study with pregnant mice that received the combination of subcutaneous administration of fluticasone propionate and oral administration of salmeterol at doses of 0/1400, 40/0, 10/200, 40/1400, or 150/10,000 mcg/kg/day (as fluticasone propionate/salmeterol) during the period of organogenesis, findings were generally consistent with the individual monoproducts and there was no exacerbation of expected fetal effects. Cleft palate, fetal death, increased implantation loss, and delayed ossification were observed in mouse fetuses when combining fluticasone propionate at a dose approximately 1.4 times the MRHDID (on a mcg/m^2 basis at a maternal subcutaneous dose of 150 mcg/kg/day) and salmeterol at a dose approximately 1470 times the MRHDID (on a mcg/m^2 basis at a maternal oral dose of 10,000 mcg/kg/day). No developmental toxicity was observed at combination doses of fluticasone propionate up to approximately 0.8 times the MRHDID (on a mcg/m^2 basis at a maternal subcutaneous dose of 40 mcg/kg) and doses of salmeterol up to approximately 420 times the MRHDID (on a mcg/m^2 basis at a maternal oral dose of 1400 mcg/kg).

Fluticasone Propionate: In embryo/fetal development studies with pregnant rats and mice dosed by the subcutaneous route throughout the period of organogenesis, fluticasone propionate was teratogenic in both species. Omphalocele, decreased body weight, and skeletal variations were observed in rat fetuses, in the presence of maternal toxicity, at a dose approximately 2 times the MRHDID (on a mcg/m^2 basis with a maternal subcutaneous dose of 100 mcg/kg/day). The rat NOAEL was observed at approximately 0.6 times the MRHDID (on a mcg/m^2 basis with a maternal subcutaneous dose of 30 mcg/kg/day). Cleft palate and fetal skeletal variations were observed in mouse fetuses at a dose approximately 0.5 times the MRHDID (on a mcg/m^2 basis with a maternal subcutaneous dose of 45 mcg/kg/day). The mouse NOAEL was observed with a dose approximately 0.16 times the MRHDID (on a mcg/m^2 basis with a maternal subcutaneous dose of 15 mcg/kg/day).

In an embryo/fetal development study with pregnant rats dosed by the inhalation route throughout the period of organogenesis, fluticasone propionate produced decreased fetal body weights and skeletal variations, in the presence of maternal toxicity, at a dose approximately 0.5 times the MRHDID (on a mcg/m^2 basis with a maternal inhalation dose of 25.7 mcg/kg/day); however, there was no evidence of teratogenicity. The NOAEL was observed with a dose approximately 0.1 times the MRHDID (on a mcg/m^2 basis with a maternal inhalation dose of 5.5 mcg/kg/day).

In an embryo/fetal development study in pregnant rabbits that were dosed by the subcutaneous route throughout organogenesis, fluticasone propionate produced reductions of fetal body weights, in the presence of maternal toxicity at doses approximately 0.02 times the MRHDID and higher (on a mcg/m^2 basis with a maternal subcutaneous dose of 0.57 mcg/kg/day). Teratogenicity was evident based upon a finding of cleft palate for 1 fetus at a dose approximately 0.2 times the MRHDID (on a mcg/m^2 basis with a maternal subcutaneous dose of 4 mcg/kg/day). The NOAEL was observed in rabbit fetuses with a dose approximately 0.004 times the MRHDID (on a mcg/m^2 basis with a maternal subcutaneous dose of 0.08 mcg/kg/day).

In a pre- and post-natal development study in pregnant rats dosed by the subcutaneous route from late gestation through delivery and lactation (Gestation Day 17 to Postpartum Day 22), fluticasone propionate was not associated with decreases in pup body weight, and had no effects on developmental landmarks, learning, memory, reflexes, or fertility at doses up to approximate equivalence to the MRHDID (on a mcg/m^2 basis with maternal subcutaneous doses up to 50 mcg/kg/day).

Fluticasone propionate crossed the placenta following subcutaneous administration to mice and rats and oral administration to rabbits.

Salmeterol: In three embryo/fetal development studies, pregnant rabbits received oral administration of salmeterol at doses ranging from 100 to 10,000 mcg/kg/day during the period of organogenesis. In pregnant Dutch rabbits administered salmeterol doses approximately 700 times the MRHDID (on a mcg/m^2 basis at maternal oral doses of 1000 mcg/kg/day and higher), fetal toxic effects were observed characteristically resulting from beta‑adrenoceptor stimulation. These included precocious eyelid openings, cleft palate, sternebral fusion, limb and paw flexures, and delayed ossification of the frontal cranial bones. No such effects occurred at a salmeterol dose approximately 420 times the MRHDID (on a mcg/m^2 basis at a maternal oral dose of 600 mcg/kg/day). New Zealand White rabbits were less sensitive since only delayed ossification of the frontal cranial bones was seen at a salmeterol dose approximately 7,000 times the MRHDID (on a mcg/m^2 basis at a maternal oral dose of 10,000 mcg/kg/day).

In two embryo/fetal development studies, pregnant rats received salmeterol by oral administration at doses ranging from 100 to 10,000 mcg/kg/day during the period of organogenesis. Salmeterol produced no maternal toxicity or embryo/fetal effects at doses up to 3500 times the MRHDID (on a mcg/m^2 basis at maternal oral doses up to 10,000 mcg/kg/day).

In a peri- and post-natal development study in pregnant rats dosed by the oral route from late gestation through delivery and lactation, salmeterol at a dose 3500 times the MRHDID (on mcg/m^2 basis with a maternal oral dose of 10,000 mcg/kg/day) was fetotoxic and decreased the fertility of survivors.

Salmeterol xinafoate crossed the placenta following oral administration to mice and rats.

8.2 Lactation

Risk Summary

There are no available data on the presence of fluticasone propionate or salmeterol in human milk, the effects on the breastfed child, or the effects on milk production. Other corticosteroids have been detected in human milk. However, fluticasone propionate and salmeterol concentrations in plasma after inhaled therapeutic doses are low and therefore concentrations in human breast milk are likely to be correspondingly low [see Clinical Pharmacology (12.3)]. The developmental and health benefits of breastfeeding should be considered along with the mother’s clinical need for AIRDUO RESPICLICK and any potential adverse effects on the breastfed child from AIRDUO RESPICLICK or from the underlying maternal condition.

Data

Animal Data

Subcutaneous administration of tritiated fluticasone propionate at a dose in lactating rats approximately 0.2 times the MRHDID for adults (on a mcg/m^2 basis) resulted in measurable levels in milk. Oral administration of salmeterol at a dose in lactating rats approximately 2900 times the MRHDID for adults (on a mcg/m^2 basis) resulted in measurable levels in milk.

8.4 Pediatric Use

The safety and effectiveness of AIRDUO RESPICLICK have been established for the treatment of asthma in pediatric patients aged 12 years and older whose asthma (1) is inadequately controlled on a long term asthma control medication or (2) warrants initiation of treatment with both an ICS and a LABA.

Use of AIRDUO RESPICLICK in pediatric patients aged 12 to 17 years for this indication is supported by evidence from two adequate and well-controlled trials in pediatric patients 12 years old and older with persistent symptomatic asthma despite ICS or ICS/LABA therapy (Trials 1 and 2) [see Clinical Studies (14)]. In these trials, 58 adolescents received AIRDUO RESPICLICK one inhalation twice daily.

The safety and effectiveness of AIRDUO RESPICLICK have not been established in pediatric patients younger than 12 years of age for the treatment of asthma. Effectiveness was not demonstrated in one adequate and well-controlled study conducted in 211 patients aged 4 to 11 years with persistent asthma on a stable asthma regimen who were treated with AIRDUO RESPICLICK 55 mcg/14 mcg one inhalation twice daily.

Effect on Growth

Inhaled corticosteroids, including fluticasone propionate, a component of AIRDUO RESPICLICK, may cause a reduction in growth velocity in adolescents [see Warning and Precautions (5.13)]. The growth of pediatric patients receiving ICS, including AIRDUO RESPICLICK, should be monitored.

If an adolescent on any corticosteroid appears to have growth suppression, the possibility that he/she is particularly sensitive to this effect of corticosteroids should be considered. In such patients, the potential growth effects of prolonged ICS treatment should be weighed against the clinical benefits obtained. To minimize the systemic effects of ICS, including AIRDUO RESPICLICK, each patient should be titrated to the lowest strength that effectively controls his/her asthma [see Dosage and Administration (2)].

8.5 Geriatric Use

No overall differences in safety or effectiveness were observed in data collected in 54 subjects aged 65 years and older versus younger subjects who were treated with AIRDUO RESPICLICK in placebo-controlled Phase 2 and 3 asthma studies.

8.6 Hepatic Impairment

Formal pharmacokinetic studies using AIRDUO RESPICLICK have not been conducted in patients with hepatic impairment. However, since both fluticasone propionate and salmeterol are predominantly cleared by hepatic metabolism [see Clinical Pharmacology (12.3)], impairment of liver function may lead to accumulation of fluticasone propionate and salmeterol in plasma. Therefore, patients with hepatic impairment should be closely monitored.

8.7 Renal Impairment

Formal pharmacokinetic studies using AIRDUO RESPICLICK have not been conducted in patients with renal impairment.

10 OVERDOSAGE

AIRDUO RESPICLICK contains both fluticasone propionate and salmeterol; therefore, the risks associated with overdosage for the individual components described below apply to AIRDUO RESPICLICK. Treatment of overdosage consists of discontinuation of AIRDUO RESPICLICK together with institution of appropriate symptomatic and/or supportive therapy. The judicious use of a cardioselective beta‑receptor blocker may be considered, bearing in mind that such medication can produce bronchospasm. Cardiac monitoring is recommended in cases of overdosage.

Fluticasone propionate

Chronic overdosage of fluticasone propionate may result in signs/symptoms of hypercorticism [see Warnings and Precautions (5.7)].

Salmeterol

The expected signs and symptoms with overdosage of salmeterol are those of excessive beta‑adrenergic stimulation and/or occurrence or exaggeration of any of the signs and symptoms of beta‑adrenergic stimulation (e.g., seizures, angina, hypertension or hypotension, tachycardia with rates up to 200 beats/min, arrhythmias, nervousness, headache, tremor, muscle cramps, dry mouth, palpitation, nausea, dizziness, fatigue, malaise, insomnia, hyperglycemia, hypokalemia, metabolic acidosis). Overdosage with salmeterol can lead to clinically significant prolongation of the QTc interval, which can produce ventricular arrhythmias.

As with all inhaled sympathomimetic medicines, cardiac arrest and even death may be associated with an overdose of salmeterol.

11 DESCRIPTION

AIRDUO RESPICLICK 55 mcg/14 mcg, AIRDUO RESPICLICK 113 mcg/14 mcg and AIRDUO RESPICLICK 232 mcg/14 mcg are combinations of fluticasone propionate and salmeterol.

Fluticasone Propionate

One active component of AIRDUO RESPICLICK is fluticasone propionate, a corticosteroid having the chemical name S-(fluoromethyl) 6α,9-difluoro-11ß,17-dihydroxy-16α-methyl-3-oxoandrosta-1,4-diene-17ß-carbothioate, 17-propionate, and the following chemical structure:

Fluticasone propionate is a white powder with a molecular weight of 500.6, and the empirical formula is C25H31F3O5S. It is practically insoluble in water, freely soluble in dimethyl sulfoxide and dimethylformamide, and slightly soluble in methanol and 95% ethanol.

Salmeterol Xinafoate

The other active component of AIRDUO RESPICLICK is salmeterol xinafoate, a beta2–adrenergic bronchodilator. Salmeterol xinafoate is the racemic form of the 1‑hydroxy‑2‑naphthoic acid salt of salmeterol. It has the chemical name 4-hydroxy-α -[[[6-(4-phenylbutoxy)hexyl]amino]methyl]-1,3-benzenedimethanol, 1-hydroxy-2-naphthalenecarboxylate and the following chemical structure:

Salmeterol xinafoate is a white powder with a molecular weight of 603.8, and the empirical formula is C25H37NO4•C11H8O3. It is freely soluble in methanol; slightly soluble in ethanol, chloroform, and isopropanol; and sparingly soluble in water.

AIRDUO RESPICLICK

AIRDUO RESPICLICK is a multidose dry powder inhaler (MDPI) for oral inhalation only. It contains fluticasone propionate, salmeterol xinafoate, and lactose monohydrate (which may contain milk proteins). The opening of the mouthpiece cover meters 5.5 mg of the formulation from the device reservoir, which contains 55 mcg, 113 mcg, or 232 mcg of fluticasone propionate, and 14 mcg of salmeterol base (equivalent to 20.3 mcg of salmeterol xinafoate). Patient inhalation through the mouthpiece causes the deagglomeration and aerosolization of the drug particles as the formulation moves through the cyclone component of the device. This is followed by dispersion into the airstream.

Under standardized in vitro test conditions, the AIRDUO RESPICLICK inhaler delivers 49 mcg, 100 mcg, or 202 mcg of fluticasone propionate and 12.75 mcg of salmeterol base (equivalent to 18.5 mcg of salmeterol xinafoate), with lactose from the mouthpiece when tested at a flow rate of 85 L/min for 1.4 seconds.

The amount of drug delivered to the lung will depend on patient factors such as inspiratory flow profiles. In adult subjects (N=50, aged 18 to 45 years) with asthma, mean peak inspiratory flow (PIF) through the AIRDUO RESPICLICK inhaler was 108.28 L/min (range: 70.37 to 129.24 L/min). In adolescent subjects (N=50, aged 12 to 17 years) with asthma, mean peak inspiratory flow (PIF) through the AIRDUO RESPICLICK inhaler was 106.72 L/min (range: 73.64 to 125.51 L/min).

12 CLINICAL PHARMACOLOGY

12.1 Mechanism of Action

AIRDUO RESPICLICK: AIRDUO RESPICLICK contains both fluticasone propionate and salmeterol. The mechanisms of action described below for the individual components apply to AIRDUO RESPICLICK. These drugs represent 2 different classes of medications (a synthetic corticosteroid and a LABA) that have different effects on clinical, physiologic, and inflammatory indices.

Fluticasone Propionate: Fluticasone propionate is a synthetic trifluorinated corticosteroid with anti-inflammatory activity. Fluticasone propionate has been shown in vitro to exhibit a binding affinity for the human glucocorticoid receptor that is 18 times that of dexamethasone, almost twice that of beclomethasone-17-monopropionate (BMP), the active metabolite of beclomethasone dipropionate, and over 3 times that of budesonide. Data from the McKenzie vasoconstrictor assay in humans are consistent with these results. The clinical significance of these findings is unknown.

Inflammation is an important component in the pathogenesis of asthma. Corticosteroids have been shown to have a wide range of actions on multiple cell types (e.g., mast cells, eosinophils, neutrophils, macrophages, and lymphocytes) and mediators (e.g., histamine, eicosanoids, leukotrienes, and cytokines) involved in inflammation. These anti-inflammatory actions of corticosteroids contribute to their efficacy in the treatment of asthma.

Salmeterol: Salmeterol is a selective LABA. In vitro studies show salmeterol to be at least 50 times more selective for beta2‑adrenoceptors than albuterol. Although beta2‑adrenoceptors are the predominant adrenergic receptors in bronchial smooth muscle and beta1‑adrenoceptors are the predominant receptors in the heart, there are also beta2‑adrenoceptors in the human heart comprising 10% to 50% of the total beta‑adrenoceptors. The precise function of these receptors has not been established, but their presence raises the possibility that even selective beta2‑agonists may have cardiac effects.

The pharmacologic effects of beta2‑adrenoceptor agonist drugs, including salmeterol, are at least in part attributable to stimulation of intracellular adenyl cyclase, the enzyme that catalyzes the conversion of adenosine triphosphate (ATP) to cyclic-3′,5′-adenosine monophosphate (cyclic AMP). Increased cyclic AMP levels cause relaxation of bronchial smooth muscle and inhibition of release of mediators of immediate hypersensitivity from cells, especially from mast cells.

In vitro tests show that salmeterol is a potent and long‑lasting inhibitor of the release of mast cell mediators, such as histamine, leukotrienes, and prostaglandin D2, from human lung. Salmeterol inhibits histamine‑induced plasma protein extravasation and inhibits platelet‑activating factor‑induced eosinophil accumulation in the lungs of guinea pigs when administered by the inhaled route. In humans, single doses of salmeterol administered via inhalation aerosol attenuate allergen‑induced bronchial hyperresponsiveness.

12.2 Pharmacodynamics

Hypothalamic Pituitary Adrenal Axis Effects (HPA)

There are no HPA data from controlled trials of the AIRDUO RESPICLICK in healthy subjects or subjects with asthma.

Cardiovascular Effects and Effects on Potassium and Glucose

AIRDUO RESPICLICK in Healthy Subjects

There were no clinical trials conducted with AIRDUO RESPICLICK that assessed cardiovascular (CV) effects in healthy subjects.

Other Fluticasone Propionate and Salmeterol Dry Powder Inhaler (DPI) Products in Healthy Subjects

Since systemic pharmacodynamic effects of salmeterol are not normally seen at the maximum approved salmeterol dosage, higher doses were used to produce measurable effects. Four trials were conducted with healthy adult subjects to assess CV effects:

1. Single‑dose crossover trial using 2 inhalations of fluticasone propionate and salmeterol DPI (500 mcg/50 mcg) (two times the maximum approved salmeterol dosage for that DPI per dosing interval), fluticasone propionate DPI 500 mcg and salmeterol DPI 50 mcg given concurrently, or fluticasone propionate DPI 500 mcg given alone,
2. Cumulative dose trial using 50 to 400 mcg of salmeterol DPI (1 time to 8 times the maximum approved salmeterol dosage per dosing interval for that DPI, respectively) given alone, or fluticasone propionate and salmeterol DPI (500 mcg/50 mcg),
3. Repeat‑dose trial for 11 days using 2 inhalations twice daily of fluticasone propionate and salmeterol DPI (250 mcg/50 mcg) (two times the maximum approved salmeterol dosage for that DPI per dosing interval), fluticasone propionate DPI 250 mcg, or salmeterol DPI 50 mcg, and
4. Single-dose trial using 5 inhalations of fluticasone propionate and salmeterol DPI (100 mcg/50 mcg) (five times the maximum approved salmeterol dosage for that DPI per dosing interval), fluticasone propionate DPI 100 mcg alone, or placebo.
  In these trials, no significant differences were observed in the pharmacodynamic effects of salmeterol (pulse rate, blood pressure, QTc interval, potassium, and glucose) whether the salmeterol was given as fluticasone propionate and salmeterol DPI, concurrently with fluticasone propionate from separate inhalers, or as salmeterol alone. The systemic pharmacodynamic effects of salmeterol were not altered by the presence of fluticasone propionate in the fluticasone propionate and salmeterol DPI product.
  Other Salmeterol Products in Subjects with Asthma:
  Inhaled salmeterol, like other beta‑adrenergic agonist drugs, can produce dose‑related CV effects and effects on blood glucose and/or serum potassium [see Warnings and Precautions (5.11, 5.17)]. The CV effects (heart rate, blood pressure) associated with salmeterol inhalation aerosol occurred with similar frequency, and are of similar type and severity, as those noted following albuterol administration.
  The effects of rising inhaled doses of salmeterol and standard inhaled doses of albuterol were studied in volunteers and in subjects with asthma. Salmeterol doses up to 84 mcg administered as inhalation aerosol resulted in heart rate increases of 3 to 16 beats/minute, about the same as albuterol dosed at 180 mcg by inhalation aerosol (4 to 10 beats/minute). Adult and adolescent subjects receiving 50 mcg doses of salmeterol MDPI (N=60) underwent continuous electrocardiographic monitoring during two 12‑hour periods after the first dose and after 1 month of therapy, and no clinically significant dysrhythmias were noted.
  Concomitant Use of AIRDUO RESPICLICK With Other Respiratory Medications:
  Short-Acting Beta2‑Agonists: In clinical trials in subjects with asthma, the mean daily need for albuterol by 166 adult and adolescent subjects aged 12 years and older using another fluticasone propionate/salmeterol DPI product was approximately 1.3 inhalations/day and ranged from 0 to 9 inhalations/day (0 to about 4.5 times the maximum approved salmeterol dosage for that DPI per dosing interval). Five percent (5%) of subjects using another fluticasone propionate/salmeterol DPI product in these trials averaged 6 or more inhalations per day (3 times the maximum approved salmeterol dosage for that DPI per dosing interval) over the course of the 12-week trials. No increase in frequency of CV adverse events was observed among subjects who averaged 6 or more inhalations per day.

Methylxanthines: In clinical trials in subjects with asthma, 39 subjects receiving another fluticasone propionate/salmeterol MDPI product, fluticasone propionate 100 mcg and salmeterol 50 mcg, fluticasone propionate 250 mcg and salmeterol 50 mcg, or fluticasone propionate 500 mcg and salmeterol 50 mcg twice daily concurrently with a theophylline product had adverse event rates similar to those in 304 subjects receiving another fluticasone propionate/salmeterol product without theophylline. Similar results were observed in subjects receiving salmeterol 50 mcg plus fluticasone propionate 500 mcg twice daily concurrently with a theophylline product (n = 39) or without theophylline (n = 132).

12.3 Pharmacokinetics

Absorption

Fluticasone Propionate:

AIRDUO RESPICLICK acts locally in the lung; therefore, plasma levels may not predict therapeutic effect. Trials using oral dosing of labeled and unlabeled drug have demonstrated that the oral systemic bioavailability of fluticasone propionate was negligible (<1%), primarily due to incomplete absorption and presystemic metabolism in the gut and liver. In contrast, the majority of the fluticasone propionate delivered to the lung was systemically absorbed.

After administration of 232 mcg/14 mcg AIRDUO RESPICLICK to patients aged 12 years and older with persistent asthma in a clinical trial, the mean Cmax value of fluticasone propionate was 66 pg/mL with a median tmax value of approximately 2 hours.

Salmeterol:

After administration of 232 mcg/14 mcg AIRDUO RESPICLICK to patients aged 12 years and older with persistent asthma, the mean Cmax values of salmeterol was 60 pg/mL. The median tmax was 5 minutes.

Distribution

Fluticasone Propionate:

Following intravenous administration, the initial disposition phase for fluticasone propionate was rapid and consistent with its high lipid solubility and tissue binding. The volume of distribution averaged 4.2 L/kg.

The percentage of fluticasone propionate bound to human plasma proteins averages 99%. Fluticasone propionate is weakly and reversibly bound to erythrocytes and is not significantly bound to human transcortin.

Salmeterol:

Volume of distribution data are not available for salmeterol.

The percentage of salmeterol bound to human plasma proteins averages 96% in vitro over the concentration range of 8 to 7,722 ng of salmeterol base per milliliter, much higher concentrations than those achieved following therapeutic doses of salmeterol.

Elimination

Fluticasone Propionate:

Following intravenous dosing, fluticasone propionate showed polyexponential kinetics and had a terminal elimination half-life of approximately 7.8 hours. Terminal half-life estimates of fluticasone propionate following oral inhalation administration of AIRDUO RESPICLICK were approximately 10.8 hours.

Metabolism

The total clearance of fluticasone propionate is high (average, 1,093 mL/minute), with renal clearance accounting for less than 0.02% of the total. The only circulating metabolite detected in humans is the 17β carboxylic acid derivative of fluticasone propionate, which is formed through the CYP3A4 pathway. This metabolite has less affinity (approximately 1/2,000) than the parent drug for the glucocorticoid receptor of human lung cytosol in vitro and negligible pharmacological activity in animal studies. Other metabolites detected in vitro using cultured human hepatoma cells have not been detected in humans.

Excretion

Less than 5% of a radiolabeled oral dose was excreted in the urine as metabolites, with the remainder excreted in the feces as parent drug and metabolites.

Salmeterol:

Terminal half-life estimates for salmeterol for AIRDUO RESPICLICK were approximately 12.6 hours.

The xinafoate moiety has no apparent pharmacologic activity. The xinafoate moiety is highly protein bound (greater than 99%) and has a long elimination half-life of 11 days.

Metabolism

Salmeterol base is extensively metabolized by hydroxylation.

An in vitro study using human liver microsomes showed that salmeterol is extensively metabolized to α hydroxysalmeterol (aliphatic oxidation) by CYP3A4. Ketoconazole, a strong inhibitor of CYP3A4, essentially completely inhibited the formation of α hydroxysalmeterol in vitro.

Excretion

In 2 healthy adult subjects who received 1 mg of radiolabeled salmeterol (as salmeterol xinafoate) orally, approximately 25% and 60% of the radiolabeled salmeterol was eliminated in urine and feces, respectively, over a period of 7 days.

Specific Populations

A population pharmacokinetic analysis was performed for fluticasone propionate and salmeterol utilizing data from 9 controlled clinical trials that included 350 subjects with asthma aged 4 to 77 years who received treatment with another fluticasone propionate and salmeterol MDPI product, the combination of HFA‑propelled fluticasone propionate and salmeterol inhalation aerosol, fluticasone propionate MDPI, HFA‑propelled fluticasone propionate inhalation aerosol, or CFC‑propelled fluticasone propionate inhalation aerosol. The population pharmacokinetic analyses for fluticasone propionate and salmeterol showed no clinically relevant effects of age, gender, race, body weight, body mass index, or percent of predicted FEV1 on apparent clearance and apparent volume of distribution. AIRDUO RESPICLICK is not approved in pediatric patients younger than 12 years.

Age: No pharmacokinetic studies have been performed with AIRDUO RESPICLICK in geriatric patients.

Adolescents Aged 12 to 17 Years: A subgroup analysis was conducted to compare patients aged 12 to 17 (n=15) and ≥18 (n=23) years following administration of 232 mcg/14 mcg AIRDUO RESPICLICK. No overall differences in fluticasone propionate and salmeterol pharmacokinetics were observed.

Male and Female Patients: A subgroup analysis was conducted to compare male (n=21) and female (n=16) adolescent and adult patients following administration of 232 mcg/14 mcg AIRDUO RESPICLICK. No overall differences in fluticasone propionate and salmeterol pharmacokinetics were observed.

Patients with Renal Impairment: The effect of renal impairment of the pharmacokinetics of AIRDUO RESPICLICK has not been evaluated.

Patients with Hepatic Impairment: Formal pharmacokinetic studies using AIRDUO RESPICLICK have not been conducted in patients with hepatic impairment. However, since both fluticasone propionate and salmeterol are predominantly cleared by hepatic metabolism, impairment of liver function may lead to accumulation of fluticasone propionate and salmeterol in plasma [see Use in Specific Populations (8.6)].

Drug Interaction Studies

In a single-dose trial, the presence of salmeterol did not alter fluticasone propionate exposure.

No studies have been performed with AIRDUO RESPICLICK to investigate the effect of fluticasone propionate on salmeterol pharmacokinetics when given in combination.

Drug Interaction Studies with Another Fluticasone Propionate/Salmeterol MDPI Product:

The population pharmacokinetic analysis from 9 controlled clinical trials in 350 subjects with asthma showed no significant effects on fluticasone propionate or salmeterol pharmacokinetics following co-administration with beta2-agonists, corticosteroids, antihistamines, or theophyllines.

Strong CYP3A4 Inhibitors: Fluticasone propionate is a substrate of CYP3A4. Coadministration of fluticasone propionate and ritonavir, a strong CYP3A4 inhibitor, is not recommended based upon a multiple-dose, crossover drug interaction trial in 18 healthy subjects [see Drug Interactions (7.1)]. Plasma fluticasone propionate concentrations following fluticasone propionate aqueous nasal spray alone were undetectable (<10 pg/mL) in most subjects, and when concentrations were detectable, peak levels (Cmax) averaged 11.9 pg/mL (range: 10.8 to 14.1 pg/mL) and AUC0-τ averaged 8.43 pg•h/mL (range: 4.2 to 18.8 pg•h/mL). However, the fluticasone propionate Cmax and AUC0-τ increased to 318 pg/mL (range: 110 to 648 pg/mL) and 3,102.6 pg•h/mL (range: 1,207.1 to 5,662.0 pg•h/mL), respectively, after 7 days of coadministration of ritonavir (100 mg twice daily) with fluticasone propionate aqueous nasal spray (200 mcg once daily). This significant increase in plasma fluticasone propionate exposure resulted in a significant decrease (86%) in serum cortisol AUC.

Ketoconazole: In a placebo-controlled crossover trial in 8 healthy adult volunteers, coadministration of a single dose of orally inhaled fluticasone propionate (1,000 mcg) with multiple doses of ketoconazole (200 mg) to steady state resulted in increased plasma fluticasone propionate exposure, a reduction in plasma cortisol AUC, and no effect on urinary excretion of cortisol.

In a placebo-controlled, crossover drug interaction trial in 20 healthy male and female subjects, coadministration of salmeterol (50 mcg twice daily) and ketoconazole, a strong CYP3A4 inhibitor, (400 mg once daily) for 7 days resulted in a significant increase in plasma salmeterol exposure as determined by a 16-fold increase in AUC (ratio with and without ketoconazole 15.76 [90% CI: 10.66, 23.31]) mainly due to increased bioavailability of the swallowed portion of the dose. Peak plasma salmeterol concentrations were increased by 1.4-fold (90% CI: 1.23, 1.68). Three (3) out of 20 subjects (15%) were withdrawn from salmeterol and ketoconazole coadministration due to beta-agonist–mediated systemic effects (2 with QTc prolongation and 1 with palpitations and sinus tachycardia). Coadministration of salmeterol and ketoconazole did not result in a clinically significant effect on mean heart rate, mean blood potassium, or mean blood glucose. Although there was no statistical effect on the mean QTc, coadministration of salmeterol and ketoconazole was associated with more frequent increases in QTc duration compared with salmeterol administration alone and placebo administration.

Erythromycin: In a multiple-dose drug interaction trial, coadministration of orally inhaled fluticasone propionate (500 mcg twice daily) and erythromycin (333 mg 3 times daily) did not affect fluticasone propionate pharmacokinetics.

In a repeat-dose trial in 13 healthy subjects, concomitant administration of erythromycin (a moderate CYP3A4 inhibitor) and salmeterol inhalation aerosol resulted in a 40% increase in salmeterol Cmax at steady state (ratio with and without erythromycin 1.4 [90% CI: 0.96, 2.03], P = 0.12), a 3.6-beat/min increase in heart rate ([95% CI: 0.19, 7.03], P<0.04), a 5.8-msec increase in QTc interval ([95% CI: -6.14, 17.77], P = 0.34), and no change in plasma potassium.

13 NONCLINICAL TOXICOLOGY

13.1 Carcinogenesis, Mutagenesis, Impairment of Fertility

Fluticasone propionate:

Fluticasone propionate demonstrated no tumorigenic potential in mice at oral doses up to 1000 mcg/kg (approximately 10 times the MRHDID for adults on a mcg/m^2 basis) for 78 weeks or in rats at inhalation doses up to 57 mcg/kg (approximately equivalent to the MRHDID for adults on a mcg/m^2 basis) for 104 weeks.

Fluticasone propionate did not induce gene mutation in prokaryotic or eukaryotic cells in vitro. No significant clastogenic effect was seen in cultured human peripheral lymphocytes in vitro or in the in vivo mouse micronucleus test.

Fertility and reproductive performance were unaffected in male and female rats at subcutaneous doses up to 50 mcg/kg (approximately equivalent to the MRHDID for adults on a mcg/m^2 basis).

Salmeterol:

In an 18‑month carcinogenicity study in CD‑mice, salmeterol at oral doses of 1400 mcg/kg and above (approximately 240 times the MRHDID on a mcg/m^2 basis) caused a dose‑related increase in the incidence of smooth muscle hyperplasia, cystic glandular hyperplasia, leiomyomas of the uterus, and ovarian cysts. No tumors were seen at 200 mcg/kg (approximately 35 times the MRHDID on a mcg/m^2 basis).

In a 24 month oral and inhalation carcinogenicity study in Sprague Dawley rats, salmeterol caused a dose related increase in the incidence of mesovarian leiomyomas and ovarian cysts at doses of 680 mcg/kg and above (approximately 240 times the MRHDID on a mcg/m^2 basis). No tumors were seen at 210 mcg/kg (approximately 75 times the MRHDID on a mcg/m^2 basis). These findings in rodents are similar to those reported previously for other beta adrenergic agonist drugs. The relevance of these findings to human use is unknown.

Salmeterol produced no detectable or reproducible increases in microbial and mammalian gene mutation in vitro. No clastogenic activity occurred in vitro in human lymphocytes or in vivo in a rat micronucleus test.

Fertility and reproductive performance were unaffected in male and female rats at oral doses up to 2000 mcg/kg (approximately 690 times the MRHDID for adults on a mcg/m^2 basis).

13.2 Animal Toxicology and/or Pharmacology

Studies in laboratory animals (minipigs, rodents, and dogs) have demonstrated the occurrence of cardiac arrhythmias and sudden death (with histologic evidence of myocardial necrosis) when beta‑agonists and methylxanthines are administered concurrently. The clinical relevance of these findings is unknown.

14 CLINICAL STUDIES

The safety and efficacy of AIRDUO RESPICLICK were evaluated in 3004 patients with asthma. The development program included 2 confirmatory trials of 12 weeks duration, a 26 week safety trial and three dose-ranging trials. The efficacy of AIRDUO RESPICLICK is based primarily on the dose-ranging trials and the confirmatory trials described below.

14.1 Dose-Ranging Studies in Patients with Asthma

Six doses of fluticasone propionate ranging from 16 mcg to 434 mcg (expressed as metered doses) administered twice daily via MDPI were evaluated in 2 randomized, double-blind, placebo-controlled 12 week trials in patients with asthma.

- Trial 201 was conducted in patients whose asthma was uncontrolled at baseline and had been treated by short-acting beta2-agonist alone or in combination with non-corticosteroid asthma medication. Low dose inhaled corticosteroids (ICS)-treated patients may have been included after a minimum of 2 weeks washout. This trial contained an open-label active comparator fluticasone propionate inhalation powder 100 mcg administered twice daily.
- Trial 202 was conducted in patients whose asthma was uncontrolled at baseline and had been treated with high dose ICS with or without a LABA. This study contained an open-label active comparator fluticasone propionate inhalation powder 250 mcg twice daily.
  The trials were dose-ranging trials of fluticasone propionate MDPI not designed to provide comparative effectiveness data and should not be interpreted as evidence of superiority/inferiority to fluticasone propionate inhalation powder. The metered doses for fluticasone MDPI (16, 28, 59, 118, 225, 434 mcg) used in Trial 201 and Trial 202 (see Figure 1) are slightly different from the metered doses for the comparator products (fluticasone inhalation powder) and the Phase 3 investigational products which are the basis of the proposed commercial labeled claim (55, 113, 232 mcg for fluticasone). The changes in doses between Phase 2 and 3 resulted from optimization of the manufacturing process.

Figure 1: Baseline Adjusted Least Square Mean Change in Trough Morning FEV1 (L) over 12 weeks (FAS)a

FAS = full analysis set; aTrials were not designed to provide comparative effectiveness data and should not be interpreted as superiority/inferiority to fluticasone propionate inhalation powder

The efficacy and safety of four doses of salmeterol xinafoate were evaluated in a double blind, 6-period crossover study compared with single dose fluticasone propionate MDPI and open label fluticasone propionate/salmeterol 100 mcg/50 mcg dry powder inhaler (DPI) as comparator in patients with persistent asthma. The trials were dose-ranging trials of the salmeterol component of AIRDUO RESPICLICK and not designed to provide comparative effectiveness data and should not be interpreted as evidence of superiority/inferiority to fluticasone propionate/salmeterol inhalation powder. The salmeterol doses studied were 6.8 mcg, 13.2 mcg, 26.8 mcg and 57.4 mcg in combination with fluticasone propionate 118 mcg delivered by MDPI (expressed as metered dose). The metered doses for salmeterol (6.8, 13.2, 26.8, 57.4 mcg) used in this study are slightly different from the metered doses for the comparator products (fluticasone/salmeterol inhalation powder) and the Phase 3 investigational products which are the basis of the proposed commercial labeled claim (55, 113, 232 mcg for fluticasone and 14 mcg for salmeterol). The phase 3 and commercial products were optimized to better match the strengths to the comparators. Plasma for pharmacokinetic characterization was obtained at each dosing period. Fluticasone propionate/salmeterol xinafoate MDPI 118 mcg/13.2 mcg had similar clinical efficacy with lower systemic exposure when compared to the 50 mcg of salmeterol in fluticasone propionate/salmeterol 100 mcg/50 mcg dry powder inhaler (Figure 2).

Figure 2: Mean Baseline Adjusted FEV1 (mL) over 12 Hours (FAS)a

FS MDPI = fluticasone propionate/salmeterol multidose dry powder inhaler; Fp MDPI = fluticasone propionate multidose dry powder inhaler; FS DPI = fluticasone propionate/salmeterol dry powder inhaler; FAS = full analysis set; FEV1 = forced expiratory volume in 1 second; aTrial was not designed to provide comparative effectiveness data and should not be interpreted as superiority/inferiority to fluticasone propionate/salmeterol inhalation powder.

14.2 Trials in the Treatment of Asthma

Adult and Adolescent Patients Aged 12 Years and Older:

Two 12-week randomized, double-blind, placebo-controlled, parallel-group, global clinical trials (Trials 1 and 2) were conducted in 1375 adult and adolescent patients (aged 12 years and older, with baseline FEV1 40% to 85% of predicted normal) with asthma that was not optimally controlled on their current therapy. Patients were randomized to receive 1 inhalation twice a day of AIRDUO RESPICLICK, fluticasone propionate MDPI alone, or placebo. Maintenance asthma therapies were discontinued at randomization.

Trial 1: In this trial, adolescents and adult patients with persistent symptomatic asthma despite low-dose or mid-dose inhaled corticosteroid (ICS) or ICS/LABA therapy were included. After completing a run-in period where patients were treated with beclomethasone dipropionate inhalation aerosol 40 mcg twice daily and a single blind placebo MDPI, the patients who met the randomization criteria were randomized to 1 inhalation twice a day of the following treatments:

- Placebo MDPI (n=130)
- Fluticasone propionate MDPI 55 mcg (n=129)
- Fluticasone propionate MDPI 113 mcg (n=130)
- AIRDUO RESPICLICK 55 mcg/14 mcg (n=129), or
- AIRDUO RESPICLICK 113 mcg/14 mcg (n=129)
  Baseline FEV1 measurements were similar across treatments: fluticasone propionate MDPI 55 mcg 2.132 L, fluticasone propionate MDPI 113 mcg 2.166 L, AIRDUO RESPICLICK 55 mcg/14 mcg 2.302 L, AIRDUO RESPICLICK 113 mcg/14 mcg 2.162 L, and placebo 2.188 L.
  The primary endpoints for this trial were the change from baseline in trough FEV1 at week 12 for all patients and standardized baseline-adjusted FEV1 AUEC0-12h at week 12 analyzed for a subset of 312 patients who performed postdose serial spirometry.
  Patients in both AIRDUO RESPICLICK treatment groups had significantly greater improvements in trough FEV1 compared with both fluticasone propionate MDPI treatment groups and the placebo group:

- AIRDUO RESPICLICK 113 mcg/14 mcg: LS mean change of 0.315 L at 12 weeks
- AIRDUO RESPICLICK 55 mcg/14 mcg: LS mean change of 0.319 L at 12 weeks
- Fluticasone propionate MDPI 113 mcg: LS mean change of 0.204 L at 12 weeks
- Fluticasone propionate MDPI 55 mcg: LS mean change of 0.172 L at 12 weeks
- Placebo: LS mean change of 0.053 L at 12 weeks
  The estimated mean differences between:

- AIRDUO RESPICLICK 55 mcg/14 mcg and AIRDUO RESPICLICK 113 mcg/14 mcg compared to placebo were 0.266 L (95% CI: 0.172, 0.360) and 0.262 L (95% CI: 0.168, 0.356), respectively.
- Fluticasone propionate MDPI 55 mcg and fluticasone propionate MDPI 113 mcg compared to placebo were 0.119 L (95% CI: 0.025, 0.212) and 0.151 L (95% CI: 0.057, 0.244), respectively.
- AIRDUO RESPICLICK 113 mcg/14 mcg and fluticasone propionate MDPI 113 mcg was 0.111 L (95% CI: 0.017, 0.206).
- AIRDUO RESPICLICK 55 mcg/14 mcg and fluticasone propionate MDPI 55 mcg was 0.147 L (95% CI: 0.053, 0.242).
  In addition, the mean FEV1 results at each visit are displayed in Figure 3.

Figure 3: Mean Change from Baseline in Trough FEV1 at Each Visit by Treatment Group Trial 1 (FAS)

FAS = full analysis set; FEV1 = forced expiratory volume in 1 second; Placebo = placebo MDPI

Supportive evidence of efficacy for AIRDUO RESPICLICK compared with placebo was derived from secondary endpoints such as the weekly average of daily trough morning peak expiratory flow and total daily use of rescue medication. The Asthma Quality of Life Questionnaire (AQLQ) for patients age ≥ 18 years or the pediatric AQLQ (PAQLQ) for patients aged 12-17 were assessed in Trial 1. The responder rate for both measures was defined as an improvement in score of 0.5 or more as threshold. In Trial 1, the responder rate for patients receiving AIRDUO RESPICLICK 55 mcg/14 mcg and AIRDUO RESPICLICK 113 mcg/14 mcg was 51% and 57% , respectively, compared to 40% for patients receiving placebo, with an odds ratio of 1.53 (95% CI: 0.93, 2.55) and 2.04 (95% CI: 1.23, 3.41), respectively.

Improvements in lung function occurred within 15 minutes of the first dose (15 minutes postdose). Compared to placebo the difference in LS mean change from baseline in FEV1 for AIRDUO RESPICLICK 55 mcg/14 mcg and 113 mcg/14 mcg was 0.216 and 0.164 L, respectively (unadjusted p-value <0.0001 for both dosages compared with placebo). Refer to Figure 4 below. Maximum improvement in FEV1 generally occurred within 3 hours for AIRDUO RESPICLICK 55 mcg/14 mcg and within 6 hours for AIRDUO RESPICLICK 113 mcg/14 mcg and improvements were sustained over the 12 hours of testing at weeks 1 and 12 (Figure 4 and Figure 5). Following the initial dose, predose FEV1 relative to day 1 baseline improved markedly over the first week of treatment and the improvement was sustained over the 12 weeks of treatment in the trial. No diminution in the 12 hour bronchodilator effect was observed with either AIRDUO RESPICLICK dose as assessed by FEV1 following 12 weeks of therapy.

Figure 4: Serial Spirometry: Mean Change from Baseline in FEV1 (L) at Day 1 by Time Point and Treatment Group Trial 1 (FAS; Serial Spirometry Subset)

FAS = full analysis set; FEV1 = forced expiratory volume in 1 second; Placebo = placebo MDPI

Figure 5: Serial Spirometry: Mean Change from Baseline in FEV1 (L) at Week 12 by Time Point and Treatment Group Trial 1 (FAS; Serial Spirometry Subset)

FAS = full analysis set; FEV1 = forced expiratory volume in 1 second; Placebo = placebo MDPI

Trial 2: In this trial, adolescents and adult patients with persistent symptomatic asthma despite inhaled corticosteroid (ICS) or ICS/LABA therapy were included. After completing a run-in period where patients were treated with single-blind fluticasone propionate MDPI 55 mcg twice daily replacing their current asthma therapy, patients who met the randomization criteria were randomized to 1 inhalation twice a day of the following treatments:

- Placebo MDPI (n=145)
- Fluticasone propionate MDPI 113 mcg (n=146)
- Fluticasone propionate MDPI 232 mcg (n=146)
- AIRDUO RESPICLICK 113 mcg/14 mcg (n=145)
- AIRDUO RESPICLICK 232 mcg/14 mcg (n=146)
  Baseline FEV1 measurements were similar across treatments: fluticasone propionate MDPI 113 mcg 2.069 L, fluticasone propionate MDPI 232 mcg 2.075 L, AIRDUO RESPICLICK 113 mcg/14 mcg 2.157 L, AIRDUO RESPICLICK 232 mcg/14 mcg 2.083 L and placebo 2.141 L.
  The primary endpoints for this trial were the change from baseline in trough FEV1 at week 12 for all patients and standardized baseline-adjusted FEV1 AUEC0-12h at week 12 analyzed for a subset of 312 patients who performed postdose serial spirometry.
  Efficacy results in this trial were similar to those observed in Trial 1. Patients in both AIRDUO RESPICLICK groups had significantly greater improvements in trough FEV1 compared with the fluticasone propionate MDPI groups and the placebo group:

- AIRDUO RESPICLICK 113 mcg/14 mcg: LS mean change of 0.271 L at 12 weeks
- AIRDUO RESPICLICK 232 mcg/14 mcg: LS mean change of 0.272 L at 12 weeks
- Fluticasone propionate MDPI 113 mcg: LS mean change of 0.119 L at 12 weeks
- Fluticasone propionate MDPI 232 mcg: LS mean change of 0.179 L at 12 weeks, and
- Placebo: LS mean change of -0.004 L at 12 weeks.
  Estimated mean differences between:

- AIRDUO RESPICLICK 113 mcg/14 mcg and AIRDUO RESPICLICK 232 mcg/14 mcg compared to placebo were 0.274 L (95% CI: 0.189, 0.360) and 0.276 L (95% CI: 0.191, 0.361), respectively.
- Fluticasone propionate MDPI 113 mcg and fluticasone propionate MDPI 232 mcg compared to placebo were 0.123 L (95% CI: 0.038, 0.208) and 0.183 L (95% CI: 0.098, 0.268), respectively.
- AIRDUO RESPICLICK 232 mcg/14 mcg and fluticasone propionate MDPI 232 mcg was 0.093 L (95% CI: 0.009, 0.178).
- AIRDUO RESPICLICK 113 mcg/14 mcg and fluticasone propionate MDPI 113 mcg was 0.152 L (95% CI: 0.066, 0.237).
  In addition, the mean FEV1 results at each visit are displayed in Figure 6.

Figure 6: Mean Change from Baseline in Trough FEV1 at Each Visit by Treatment Group Trial 2 (FAS)

FAS = full analysis set; FEV1 = forced expiratory volume in 1 second; Placebo = placebo MDPI

Supportive evidence of efficacy for AIRDUO RESPICLICK compared with placebo was derived from secondary endpoints such as the weekly average of daily trough morning peak expiratory flow and total daily use of rescue medication. There were fewer withdrawals due to worsening asthma in patients treated with AIRDUO RESPICLICK than with placebo. The AQLQ for patients age ≥ 18 years or the PAQLQ for patients aged 12-17 were assessed in Trial 2. The responder rate for both measures was defined as an improvement in score of 0.5 or more as threshold. In Trial 2, the responder rate for patients receiving AIRDUO RESPICLICK 113 mcg/14 mcg and AIRDUO RESPICLICK 232 mcg/14 mcg was 48% and 41%, respectively, compared to 27% for patients receiving placebo, with an odds ratio of 2.59 (95% CI: 1.56, 4.31) and 1.94 (95% CI: 1.16, 3.23), respectively.

Improvements in lung function occurred within 15 minutes of the first dose (15 minutes postdose). Compared with placebo, for AIRDUO RESPICLICK 113 mcg/14 mcg and 232 mcg/14 mcg the difference in LS mean change from baseline in FEV1 was 0.160 L and 0.187 L, respectively (unadjusted p-value <0.0001 for both doses compared with placebo). Maximum improvement in FEV1 generally occurred within 3 hours for both AIRDUO RESPICLICK dose groups, and improvements were sustained over the 12 hours of testing at weeks 1 and 12 (Figure 7 and Figure 8). Following the initial dose, predose FEV1 relative to day 1 baseline improved markedly over the first week of treatment and the improvement was sustained over the 12 weeks of treatment in the trial. No diminution in the 12 hour bronchodilator effect was observed with either AIRDUO RESPICLICK dose as assessed by FEV1 following 12 weeks of therapy.

Figure 7: Serial Spirometry: Mean Change from Baseline in FEV1 (L) at Day 1 by Time Point and Treatment Group Trial 2 (FAS; Serial Spirometry Subset)

FAS = full analysis set; FEV1 = forced expiratory volume in 1 second; Placebo = placebo MDPI

Figure 8: Serial Spirometry: Mean Change from Baseline in FEV1 (L) at Week 12 by Time Point and Treatment Group Trial 2 (FAS; Serial Spirometry Subset)

FAS = full analysis set; FEV1 = forced expiratory volume in 1 second; Placebo = placebo MDPI

16 HOW SUPPLIED/STORAGE AND HANDLING

How Supplied

AIRDUO RESPICLICK inhalation powder:

- a multidose, dry-powder inhaler (MDPI)
- each inhaler is white, has a yellow cap and is packaged individually in a foil pouch with a dessicant, each pouch is packed in a carton
- each inhaler contains 0.45 grams of the formulation and provides 60 actuations
- available in 3 strengths

STRENGTH | NDC CODE
AIRDUO RESPICLICK 55 mcg/14 mcg (low) | NDC 59310-805-06
AIRDUO RESPICLICK 113 mcg/14 mcg (medium) | NDC 59310-812-06
AIRDUO RESPICLICK 232 mcg/14 mcg (high) | NDC 59310-822-06

Each AIRDUO RESPICLICK inhaler has a dose counter attached to the actuator. Patients should never try to alter the numbers for the dose counter. Discard the inhaler when the counter displays 0, 30 days after opening the foil pouch or after the expiration date on the product, whichever comes first. The labeled amount of medication in each actuation cannot be assured after the counter displays 0, even though the inhaler is not completely empty and will continue to operate [see Patient Counseling Information (17)].

Storage and Handling

Store at room temperature (between 15ºC and 25ºC; 59ºF and 77ºF) in a dry place; excursions permitted from 59º F to 86º F (15ºC to 30ºC). Avoid exposure to extreme heat, cold, or humidity.

Store AIRDUO RESPICLICK inside the unopened moisture‑protective foil pouch until initial use. Discard AIRDUO RESPICLICK 30 days after opening the foil pouch or when the counter reads 0, whichever comes first. The inhaler is not reusable. Do not attempt to take the inhaler apart.

17 PATIENT COUNSELING INFORMATION

Advise the patient to read the FDA-approved patient labeling (Patient Information and Instructions for Use).

Patients should be given the following information:

Serious Asthma Events

Inform patients with asthma that LABA when used alone increases the risk of asthma-related hospitalization and asthma-related death. Available data show that when ICS and LABA are used together, such as with AIRDUO RESPICLICK, there is not a significant increase in the risk of these events [see Warnings and Precautions (5.1)].

Not for Acute Symptoms

Inform patients that AIRDUO RESPICLICK is not meant to relieve acute asthma symptoms and extra doses should not be used for that purpose. Advise patients to treat acute asthma symptoms with an inhaled, short‑acting beta2‑agonist such as albuterol. Provide patients with such medication and instruct them in how it should be used. [see Warmings and Precautions (5.2)].

Instruct patients to seek medical attention if they experience any of the following:

- Decreasing effectiveness of inhaled, short‑acting beta2‑agonists
- Need for more inhalations than usual of inhaled, short‑acting beta2‑agonists
- Significant decrease in lung function as outlined by the physician

Tell patients they should not stop therapy with AIRDUO RESPICLICK without physician/provider guidance since symptoms may recur after discontinuation.

Avoid Use Additional Long-Acting Beta2‑Agonists

Instruct patients not to use other LABA for asthma [see Warnings and Precautions (5.3)].

Oropharyngeal Candidiasis

Inform patients that localized infections with Candida albicans occurred in the mouth and pharynx in some patients. If oropharyngeal candidiasis develops, treat it with appropriate local or systemic (i.e., oral) antifungal therapy while still continuing therapy with AIRDUO RESPICLICK, but at times therapy with AIRDUO RESPICLICK may need to be temporarily interrupted under close medical supervision. Rinsing the mouth with water without swallowing after inhalation is advised to help reduce the risk of thrush [see Warnings and Precautions (5.4)].

Immunosuppression and Infections

Warn patients who are on immunosuppressant doses of corticosteroids to avoid exposure to chickenpox or measles and, if exposed, to consult their physicians without delay. Inform patients of potential worsening of existing tuberculosis, fungal, bacterial, viral, or parasitic infections; or ocular herpes simplex [see Warnings and Precautions (5.5)].

Hypercorticism and Adrenal Suppression

Advise patients that AIRDUO RESPICLICK may cause systemic corticosteroid effects of hypercorticism and adrenal suppression. Additionally, inform patients that deaths due to adrenal insufficiency have occurred during and after transfer from systemic corticosteroids. Patients should taper slowly from systemic corticosteroids if transferring to AIRDUO RESPICLICK [see Warnings and Precautions (5.7)].

Immediate Hypersensitivity Reactions

Advise patients that immediate hypersensitivity reactions (e.g., urticaria, angioedema, rash, bronchospasm, hypotension), including anaphylaxis, may occur after administration of AIRDUO RESPICLICK. Patients should discontinue AIRDUO RESPICLICK if such reactions occur and contact their healthcare provider or get emergency medical help. There have been reports of anaphylactic reactions in patients with severe milk protein allergy after inhalation of powder products containing lactose; therefore, patients with severe milk protein allergy should not take AIRDUO RESPICLICK [see Warnings and Precautions (5.10)].

Reduction in Bone Mineral Density

Advise patients who are at an increased risk for decreased BMD that the use of corticosteroids may pose an additional risk [see Warnings and Precautions (5.12)].

Reduced Growth Velocity

Inform patients that orally inhaled corticosteroids, including fluticasone propionate, may cause a reduction in growth velocity when administered to adolescent patients. Physicians should closely follow the growth of adolescents taking corticosteroids by any route [see Warnings and Precautions (5.13)].

Ocular Effects

Long-term use of inhaled corticosteroids may increase the risk of some eye problems (cataracts or glaucoma); consider regular eye examinations [see Warnings and Precautions (5.14)].

Risks Associated with Beta‑Agonist Therapy

Inform patients of adverse effects associated with beta2‑agonists, such as palpitations, chest pain, rapid heart rate, tremor, or nervousness [see Warnings and Precautions (5.11)].

Pregnancy

Inform patients who are pregnant or nursing that they should contact their physician about the use of AIRDUO RESPICLICK [see Use in Specific Populations (8.1)].

Use Daily for Best Effect

Patients should use AIRDUO RESPICLICK at regular intervals as directed. The daily dosage of AIRDUO RESPICLICK should not exceed 1 inhalation twice a day. Advise patients, if they miss a dose, to take their next dose at the same time they normally do and to not take 2 doses at one time. Individual patients will experience a variable time to onset and degree of symptom relief and full benefit may not be achieved until treatment has been administered for 1 to 2 weeks or longer. Patients should not increase the prescribed dosage but should contact their physicians if symptoms do not improve or if the condition worsens. Instruct patients not to stop use of AIRDUO RESPICLICK abruptly. Patients should contact their physicians immediately if they discontinue use of AIRDUO RESPICLICK.

Dose Counter

Instruct patients that AIRDUO RESPICLICK has a dose counter that displays the number of actuations (inhalations) left in the inhaler. When the patient receives a new inhaler, the number 60 will be displayed. The dose counter will count down each time the mouthpiece is opened and closed. When the dose counter reaches 20, the color of the numbers will change to red to remind the patient to contact their pharmacist or healthcare provider for a refill of their medication. When the dose counter reaches 0, the patient should stop using the inhaler, and dispose of it in accordance with state and local regulations.

Caring for and Storing the Inhaler

Instruct patients to not open their inhaler unless they are taking a dose. Repeated opening and closing the cover without taking medication will waste medication and may damage the inhaler.

Advise patients to keep their inhaler dry and clean at all times. Never wash or put any part of the inhaler in water. Patient should replace inhaler if washed or placed in water. Advise patients to immediately replace inhaler if mouthpiece cover is damaged or broken.

Gently wipe the mouthpiece with a dry cloth or tissue as needed.

Instruct patients to store the inhaler at room temperature and to avoid exposure to extreme heat, cold, or humidity.

Instruct patients to never take the inhaler apart.

Inform patients to discard AIRDUO RESPICLICK when the dose counter displays 0, 30 days after opening the foil pouch or after the expiration date on the product, whichever comes first.

Distributed by:

Teva Pharmaceuticals USA, Inc.

Parsippany, NJ 07054
©2021 Teva Respiratory, LLC. All rights reserved.

United States Patent Nos. 6701917, 6718972, 6748947, 6871646, 7540282, 8006690, 8651103, 8714149, 8978966, 9066957, 9216260, 9415008, 9463288, 9616024, 9731087, 9987229, 10022510, 10124131, 10195375, 10561808, 10765820.

AIRDPI-006

Revised: July 2021

PATIENT INFORMATION

AIRDUO® RESPICLICK® (ayr´ due oh res-pē-klik)

(fluticasone propionate and salmeterol) inhalation powder 55 mcg/14 mcg

AIRDUO® RESPICLICK® (ayr´ due oh res-pē-klik)

(fluticasone propionate and salmeterol) inhalation powder 113 mcg/14 mcg

AIRDUO® RESPICLICK® (ayr´ due oh res-pē-klik)

(fluticasone propionate and salmeterol) inhalation powder 232 mcg/14 mcg

for oral inhalation use

What is AIRDUO RESPICLICK?

- AIRDUO RESPICLICK combines the inhaled corticosteroid (ICS) medicine fluticasone propionate and the LABA medicine salmeterol.
- ICS medicines such as fluticasone propionate help to decrease inflammation in the lungs. Inflammation in the lungs can lead to breathing problems.
- LABA medicines such as salmeterol help the muscles around the airways in your lungs stay relaxed to prevent symptoms, such as wheezing, cough, chest tightness, and shortness of breath. These symptoms can happen when the muscles around the airways tighten. This makes it hard to breathe.
- AIRDUO RESPICLICK is a prescription medicine used to control symptoms of asthma and to prevent symptoms such as wheezing in people 12 years of age and older.
- AIRDUO RESPICLICK contains salmeterol. LABA medicines such as salmeterol when used alone increase the risk of hospitalizations and death from asthma problems. AIRDUO RESPICLICK contains an ICS and a LABA. When an ICS and LABA are used together, there is not a significant increased risk in hospitalizations and death from asthma problems.
- AIRDUO RESPICLICK is not for people 12 years of age and older with asthma who are well controlled with an asthma control medicine, such as a low or medium dose of an inhaled corticosteroid medicine. AIRDUO RESPICLICK is for people 12 years of age and older with asthma who need both an ICS and LABA medicine.
- AIRDUO RESPICLICK is not used to relieve sudden breathing problems and will not replace a rescue inhaler.

- It is not known if AIRDUO RESPICLICK is safe and effective in children younger than 12 years of age.

Do not use AIRDUO RESPICLICK:

- to treat sudden, severe symptoms of asthma.
- if you have a severe allergy to milk proteins. Ask your healthcare provider if you are not sure.

- if you are allergic to fluticasone propionate or any of the inactive ingredients in AIRDUO RESPICLICK. See the end of this leaflet for a complete list of ingredients in AIRDUO RESPICLICK.

Tell your healthcare provider about all of your medical conditions, including if you:

- have heart problems.

- have high blood pressure.
- have seizures.
- have thyroid problems.
- have diabetes.
- have liver problems.
- have weak bones (osteoporosis).
- have an immune system problem.
- have eye problems, such as glaucoma or cataracts.
- are allergic to milk proteins.
- have any type of viral, bacterial, fungal, or parasitic infection.
- are exposed to chickenpox or measles.
- are pregnant or plan to become pregnant. It is not known if AIRDUO RESPICLICK may harm your unborn baby.
- are breastfeeding. It is not known if the medicines in AIRDUO RESPICLICK pass into your breast milk and if they can harm your baby.

Tell your healthcare provider about all the medicines you take, including prescription and over-the-counter medicines, vitamins, and herbal supplements. AIRDUO RESPICLICK and certain other medicines may interact with each other. This may cause serious side effects. Especially, tell your healthcare provider if you take antifungal or anti-HIV medicines.

How should I use AIRDUO RESPICLICK?

Read the step-by-step instructions for using AIRDUO RESPICLICK at the end of this Patient Information leaflet.

- AIRDUO RESPICLICK is for oral inhalation only.
- Rinse your mouth with water without swallowing after each dose of AIRDUO RESPICLICK.
- AIRDUO RESPICLICK comes in 3 different strengths. Your healthcare provider prescribed the strength that is best for you.
- Use AIRDUO RESPICLICK exactly as your healthcare provider tells you to use it. Do not use AIRDUO RESPICLICK more often than prescribed.
- Use 1 inhalation of AIRDUO RESPICLICK 2 times each day. Use AIRDUO RESPICLICK at the same time each day, about 12 hours apart. If you miss a dose of AIRDUO RESPICLICK, just skip that dose. Take your next dose at your usual time. Do not take 2 doses at one time.
- AIRDUO RESPICLICK does not need priming. Do not use a spacer or volume holding chamber with AIRDUO RESPICLICK.
- Do not open the cap on your AIRDUO RESPICLICK inhaler until you are ready for your dose because this will waste your medicine or may damage your inhaler.
- If you take too much AIRDUO RESPICLICK, call your healthcare provider or go to the nearest hospital emergency room right away if you have any unusual symptoms, such as worsening shortness of breath, chest pain, increased heart rate, or shakiness.
- Do not use other medicines that contain a LABA for any reason. Examples of other medicines that contain a LABA include salmeterol, formoterol fumarate, arformoterol tartrate, and indacaterol. Ask your healthcare provider or pharmacist if any of your other medicines are LABA medicines.
- Do not stop using AIRDUO RESPICLICK unless told to do so by your healthcare provider because your symptoms might get worse. Your healthcare provider will change your medicines as needed.
- AIRDUO RESPICLICK does not relieve sudden asthma symptoms. You should not take extra doses of AIRDUO RESPICLICK to relieve sudden asthma symptoms. Always have a rescue inhaler with you to treat sudden asthma symptoms. If you do not have a rescue inhaler, call your healthcare provider to have one prescribed for you.
- Call your healthcare provider or get medical care right away if:
  - your breathing problems get worse.
  - you need to use your rescue inhaler more often than usual.
  - your rescue inhaler does not work as well to relieve your symptoms.
  - your peak flow meter results decrease. Your healthcare provider will tell you the numbers that are right for you.
  - you have asthma and your symptoms do not improve after using AIRDUO RESPICLICK regularly for one week.

What are the possible side effects with AIRDUO RESPICLICK?

AIRDUO RESPICLICK can cause serious side effects, including:

- fungal infection in your mouth and throat (thrush). Rinse your mouth with water without swallowing after using AIRDUO RESPICLICK to help reduce your chance of getting thrush.
- weakened immune system and increased chance of getting infections (immunosuppression).
- reduced adrenal function (adrenal insufficiency). Adrenal insufficiency is a condition where the adrenal glands do not make enough steroid hormones. This can happen when you stop taking oral corticosteroid medicines (such as prednisone) and start taking a medicine containing an inhaled steroid (such as AIRDUO RESPICLICK). When your body is under stress such as from fever, trauma (such as a car accident), infection, or surgery, adrenal insufficiency can get worse and may cause death.

Symptoms of adrenal insufficiency include:

- feeling tired
- nausea and vomiting
- lack of energy
- low blood pressure
- weakness

- sudden breathing problems immediately after inhaling your medicine. If you have sudden breathing problems immediately after inhaling your medicine, stop using AIRDUO RESPICLICK and call your healthcare provider right away.

- serious allergic reactions. Stop using AIRDUO RESPICLICK and call your healthcare provider or get emergency medical help if you get any of the following symptoms of a serious allergic reaction:
  - rash
  - swelling of your face, mouth, and tongue
  - hives
  - breathing problems
- effects on heart.
  - increased blood pressure
  - chest pain
  - a fast or irregular heartbeat
- effects on nervous system

- tremor
- nervousness

- bone thinning or weakness (osteoporosis).
- slowed growth in children. The growth of a child should be checked often.
- eye problems including glaucoma and cataracts. You should have regular eye exams while using AIRDUO RESPICLICK.
- changes in laboratory blood values (sugar, potassium, certain types of white blood cells).

Common side effects of AIRDUO RESPICLICK in patients ages 12 years and older include:

- infection of nose and throat
- back pain
- thrush in your mouth or throat. Rinse your mouth with water without swallowing after use to help prevent this.
- headache
- cough

These are not all the possible side effects of AIRDUO RESPICLICK.

Call your healthcare provider for medical advice about side effects. You may report side effects to FDA at 1-800-FDA-1088.

How should I store AIRDUO RESPICLICK?

- Store AIRDUO RESPICLICK at room temperature between 59ºF and 77ºF (15ºC and 25ºC).
- Store AIRDUO RESPICLICK in a dry place. Avoid exposure to extreme heat, cold, or humidity.
- Store AIRDUO RESPICLICK in the unopened foil pouch and only open when ready for use.
- Do not take your AIRDUO RESPICLICK apart.
- Keep the yellow cap on the inhaler closed during storage.
- Keep your AIRDUO RESPICLICK inhaler dry and clean at all times.
- Throw away AIRDUO RESPICLICK 30 days after opening the foil pouch, when the dose counter displays ‘0’, or after the expiration date on the product, whichever comes first.

Keep AIRDUO RESPICLICK and all medicines out of the reach of children.

General information about the safe and effective use of AIRDUO RESPICLICK.

Medicines are sometimes prescribed for purposes other than those listed in a Patient Information leaflet. Do not use AIRDUO RESPICLICK for a condition for which it was not prescribed. Do not give AIRDUO RESPICLICK to other people, even if they have the same symptoms that you have. It may harm them.

You can ask your healthcare provider or pharmacist for information about AIRDUO RESPICLICK that is written for health professionals.

What are the ingredients in AIRDUO RESPICLICK?

Active ingredients: fluticasone propionate, salmeterol xinafoate

Inactive ingredient: lactose monohydrate (may contain milk proteins)

Distributed by: Teva Pharmaceuticals USA, Inc.
Parsippany, NJ 07054

©2021 Teva Respiratory, LLC. All rights reserved.

For more information about AIRDUO RESPICLICK, call 1-888-482-9522 or visit our website at www.AIRDUO.com.

This Patient Information leaflet has been approved by the U.S. Food and Drug Administration.

AIRDPL-006

Revised: July 2021

INSTRUCTIONS FOR USE

AIRDUO® RESPICLICK® (ayr´due oh res-pē-klik)
(fluticasone propionate and salmeterol) inhalation powder 55 mcg/14 mcg

AIRDUO® RESPICLICK® (ayr´due oh res-pē-klik)
(fluticasone propionate and salmeterol) inhalation powder 113 mcg/14 mcg

AIRDUO® RESPICLICK® (ayr´due oh res-pē-klik)
(fluticasone propionate and salmeterol) inhalation powder 232 mcg/14 mcg

for oral inhalation use

Your AIRDUO RESPICLICK Inhaler

When you are ready to use AIRDUO RESPICLICK for the first time, remove the AIRDUO RESPICLICK inhaler from the foil pouch.

There are 2 main parts of your AIRDUO RESPICLICK inhaler including the:

- white inhaler with the mouthpiece. See Figure A.
- yellow cap that covers the mouthpiece of the inhaler. See Figure A.

There is a dose counter in the back of the inhaler with a viewing window that shows you how many doses of medicine you have left. See Figure A.

Figure A

- Your AIRDUO RESPICLICK inhaler contains 60 doses (inhalations). See Figure B.
- The dose counter shows the number of doses left in your inhaler.
- When there are 20 doses left, the color of the numbers on the dose counter will change to red and you should refill your prescription or ask your healthcare provider for another prescription.
- When the dose counter displays ‘0’ your inhaler is empty and you should stop using the inhaler and throw it away. See Figure B.

Figure B

Important:

- Always close the cap after each inhalation so your inhaler will be ready for you to take your next dose. Do not open the cap unless you are ready for your next dose.
- You will hear a “click” sound when the cap is opened all the way. If you do not hear the “click” sound the inhaler may not be activated to give you a dose of medicine.
- AIRDUO RESPICLICK does not have an activation button or medicine canister. When you open the cap, a dose of AIRDUO RESPICLICK will be activated for delivery of the medicine.
- Do not use a spacer or volume holding chamber with AIRDUO RESPICLICK. AIRDUO RESPICLICK does not need priming.

Using your AIRDUO RESPICLICK inhaler:

Important: Make sure the cap is closed before you start using your inhaler.

Step 1. Open

Figure C

- Hold the inhaler upright and open the yellow cap all the way until it “clicks”. See Figure C.
- Each time you open the yellow cap and it “clicks”, 1 dose of AIRDUO RESPICLICK is ready to be inhaled.

Remember:

- For the correct use of AIRDUO RESPICLICK, hold the inhaler upright as you open the yellow cap. See Figure D.
- Do not hold the inhaler in any other way as you open the yellow cap.
- Do not open the yellow cap until you are ready to take a dose of AIRDUO RESPICLICK.

Figure D

Step 2. Inhale

Figure E

- Before you inhale, breathe out (exhale) through your mouth and push as much air from your lungs as you can. See Figure E.
- Do not exhale into the inhaler mouthpiece.

Figure F

- Put the mouthpiece in your mouth and close your lips tightly around it. See Figure F.

Figure G

- Do not block the vent above the mouthpiece with your lips or fingers. See Figure G.
- Breathe in quickly and deeply through your mouth to deliver the dose of medicine to your lungs.
- Remove the inhaler from your mouth.
- Hold your breath for about 10 seconds or for as long as you comfortably can.
- Your AIRDUO RESPICLICK inhaler delivers your dose of medicine as a very fine powder that you may or may not taste or feel. Do not take an extra dose from the inhaler even if you do not taste or feel the medicine.

Step 3. Close

Figure H

- Close the yellow cap firmly over the mouthpiece. See Figure H.
- Make sure you close the yellow cap after each inhalation so that the inhaler will be ready for your next dose.
- Rinse your mouth with water without swallowing after each inhalation.

How should I store AIRDUO RESPICLICK?

- Store AIRDUO RESPICLICK at room temperature between 59ºF and 77ºF (15ºC and 25ºC).
- Avoid exposure to extreme heat, cold, or humidity.
- Store AIRDUO RESPICLICK in the unopened foil pouch and only open when ready for use.
- Keep the yellow cap on the inhaler closed during storage.
- Keep your AIRDUO RESPICLICK inhaler dry and clean at all times.
- Keep your AIRDUO RESPICLICK inhaler and all medicines out of the reach of children.

Cleaning your AIRDUO RESPICLICK inhaler

- Do not wash or put any part of your AIRDUO RESPICLICK inhaler in water. Replace your inhaler if washed or placed in water.
- AIRDUO RESPICLICK contains a powder and must be kept clean and dry at all times.
- You can clean the mouthpiece if needed using a dry cloth or tissue. Routine cleaning is not required.

Replacing your AIRDUO RESPICLICK inhaler

- Immediately replace your inhaler if the mouthpiece cover is damaged or broken. Never take the inhaler apart.
- The dose counter on the back of your inhaler shows how many doses you have left.
- When there are 20 doses left, the color of the numbers on the dose counter will change to red and you should refill your prescription or ask your healthcare provider for another prescription.
- When the counter displays ‘0’ your AIRDUO RESPICLICK inhaler is empty and you should stop using the inhaler and throw it away.
- Throw away AIRDUO RESPICLICK 30 days after opening the foil pouch, when the dose counter displays ‘0’, or after the expiration date on the product, whichever comes first.

Important information

- Do not open the yellow cap unless you are taking a dose. Repeatedly opening and closing the cap without inhaling a dose will waste the medicine and may damage your inhaler.
- Your AIRDUO RESPICLICK inhaler contains dry powder so it is important that you do not blow or breathe into it.

Support

- If you have any questions about AIRDUO RESPICLICK or how to use your inhaler, go to www.AIRDUORESPICLICK.com, or call 1-888-482-9522.

These Instructions for Use have been approved by the U.S. Food and Drug Administration.

Distributed by:

Teva Pharmaceuticals USA, Inc.
Parsippany, NJ 07054

©2021 Teva Respiratory, LLC. All rights reserved.

AIRDIFU-006

Revised: July 2021

Package/Label Display Panel

TEVA

NDC 59310-805-06

Rx Only

AirDuo®

RespiClick® 55/14

(fluticasone propionate 55 mcg

and salmeterol 14 mcg)

Inhalation Powder

55 mcg/14 mcg

With Dose Counter

FOR ORAL INHALATION ONLY

60 METERED INHALATIONS

0.45 g NET CONTENTS

Refer to enclosed Medication Guide and

Instructions for Use for detailed

information on product use and handling.

ATTENTION: Dispense with enclosed Medication Guide.

PC5496 AirDuo Respi 55_14

Package/Label Display Panel

TEVA

NDC 59310-812-06

Rx Only

AirDuo®

RespiClick® 113/14

(fluticasone propionate 113 mcg

and salmeterol 14 mcg)

Inhalation Powder

113 mcg/14 mcg

With Dose Counter

FOR ORAL INHALATION ONLY

60 METERED INHALATIONS

0.45 g NET CONTENTS

Refer to enclosed Medication Guide and

Instructions for Use for detailed

information on product use and handling.

ATTENTION: Dispense with enclosed Medication Guide.

PC5497 AirDuo Respi 113_14 mcg

Package/Label Display Panel

TEVA

NDC 59310-822-06

Rx Only

AirDuo®

RespiClick® 232/14

(fluticasone propionate 232 mcg

and salmeterol 14 mcg)

Inhalation Powder

232 mcg/14 mcg

With Dose Counter

FOR ORAL INHALATION ONLY

60 METERED INHALATIONS

0.45 g NET CONTENTS

Refer to enclosed Medication Guide and

Instructions for Use for detailed

information on product use and handling.

ATTENTION: Dispense with enclosed Medication Guide.

PC5498 AirDuo Respi 232_14 mcg